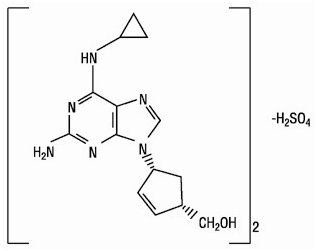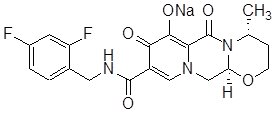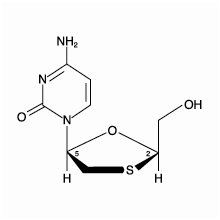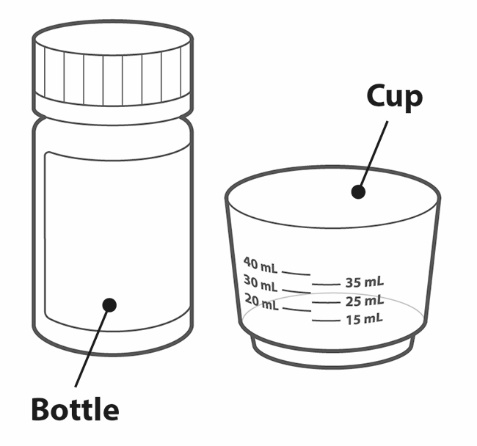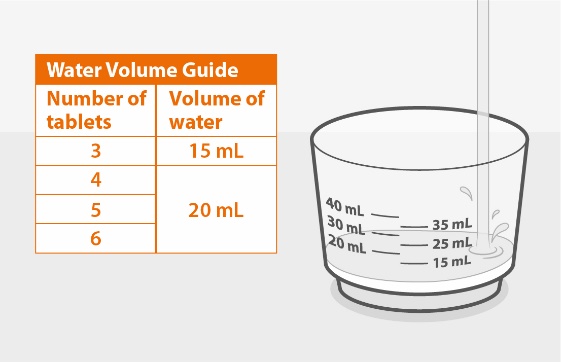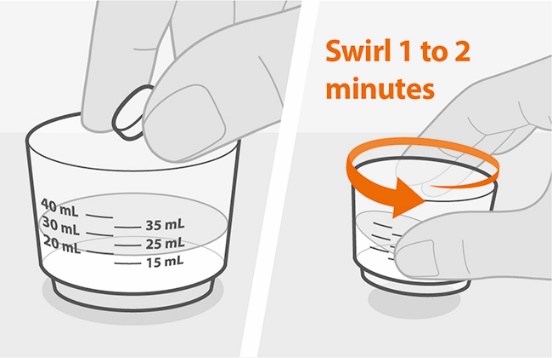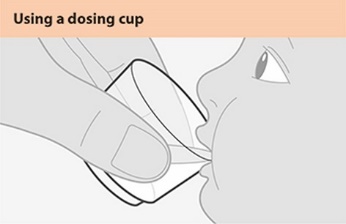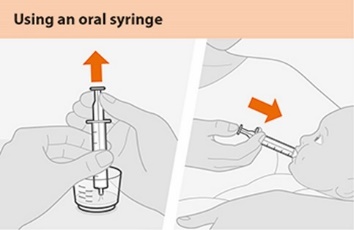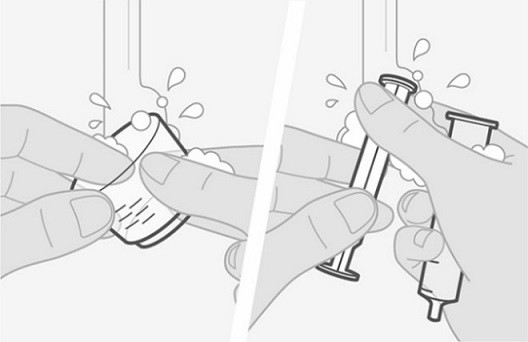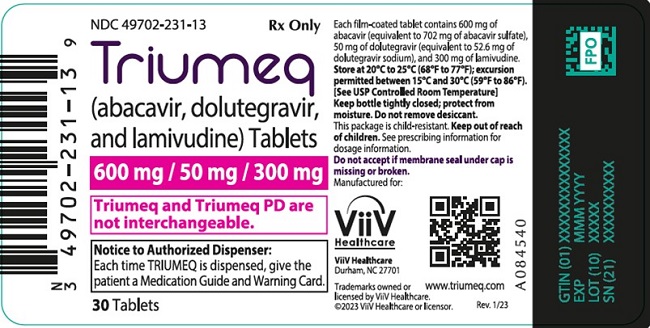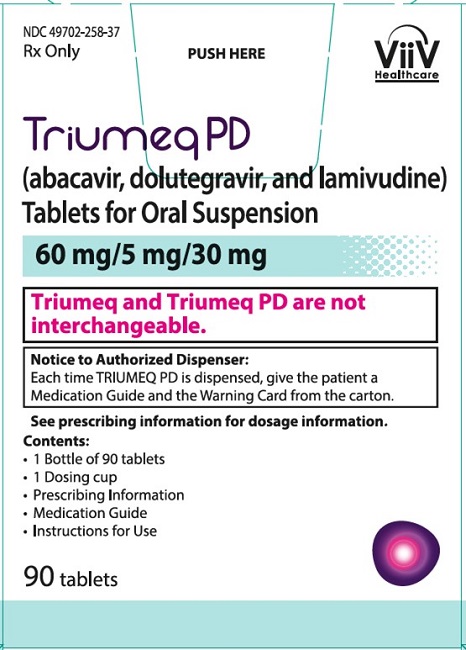 DRUG LABEL: Triumeq
NDC: 49702-231 | Form: TABLET, FILM COATED
Manufacturer: ViiV Healthcare Company
Category: prescription | Type: HUMAN PRESCRIPTION DRUG LABEL
Date: 20240708

ACTIVE INGREDIENTS: ABACAVIR SULFATE 600 mg/1 1; DOLUTEGRAVIR SODIUM 50 mg/1 1; LAMIVUDINE 300 mg/1 1
INACTIVE INGREDIENTS: MANNITOL; MAGNESIUM STEARATE; MICROCRYSTALLINE CELLULOSE; POVIDONE, UNSPECIFIED; SODIUM STARCH GLYCOLATE TYPE A CORN; FERROSOFERRIC OXIDE; FERRIC OXIDE RED; POLYETHYLENE GLYCOL, UNSPECIFIED; POLYVINYL ALCOHOL, UNSPECIFIED; TALC; TITANIUM DIOXIDE

HIGHLIGHTS OF PRESCRIBING INFORMATION

These highlights do not include all the information needed to use TRIUMEQ and TRIUMEQ PD safely and effectively. See full prescribing information for TRIUMEQ and TRIUMEQ PD.
TRIUMEQ (abacavir, dolutegravir, and lamivudine) tablets, for oral use
TRIUMEQ PD (abacavir, dolutegravir, and lamivudine) tablets for oral suspension
Initial U.S. Approval: 2014

WARNING: HYPERSENSITIVITY REACTIONS, AND EXACERBATIONS OF HEPATITIS B

See full prescribing information for complete boxed warning.

Hypersensitivity Reactions

- Serious and sometimes fatal hypersensitivity reactions have occurred with abacavir-containing products. (5.1)
- Hypersensitivity to abacavir is a multi-organ clinical syndrome. (5.1)
- Patients who carry the HLA‑B*5701 allele are at a higher risk of experiencing a hypersensitivity reaction to abacavir. (5.1)
- TRIUMEQ and TRIUMEQ PD are contraindicated in patients with a prior hypersensitivity reaction to abacavir and in HLA-B*5701-positive patients. (4)
- Discontinue TRIUMEQ or TRIUMEQ PD as soon as a hypersensitivity reaction is suspected. Regardless of HLA-B*5701 status, permanently discontinue TRIUMEQ or TRIUMEQ PD if hypersensitivity cannot be ruled out, even when other diagnoses are possible. (5.1)
- Following a hypersensitivity reaction to TRIUMEQ or TRIUMEQ PD, NEVER restart TRIUMEQ, TRIUMEQ PD, or any other abacavir‑containing product. (5.1)

Exacerbations of Hepatitis B

- All patients with HIV-1 should be tested for the presence of hepatitis B virus (HBV) prior to or when initiating TRIUMEQ or TRIUMEQ PD. Emergence of lamivudine-resistant HBV variants associated with lamivudine-containing antiretroviral regimens has been reported. If TRIUMEQ or TRIUMEQ PD is used in patients co-infected with HIV-1 and HBV, additional treatment should be considered for appropriate treatment of chronic HBV; otherwise, consider an alternative regimen.
- Severe acute exacerbations of HBV have been reported in patients who are co-infected with HBV and HIV‑1 and have discontinued lamivudine, a component of TRIUMEQ and TRIUMEQ PD. Closely monitor hepatic function in these patients and, if appropriate, initiate anti-HBV treatment. (5.2)

1 INDICATIONS AND USAGE

TRIUMEQ and TRIUMEQ PD are a combination of dolutegravir (integrase strand transfer inhibitor [INSTI]), abacavir, and lamivudine (both nucleoside analogue reverse transcriptase inhibitors) indicated for the treatment of HIV-1 infection in adults and in pediatric patients aged at least 3 months and weighing at least 6 kg. (1)

Limitations of Use:

TRIUMEQ and TRIUMEQ PD alone are not recommended in patients with resistance-associated integrase substitutions or clinically suspected INSTI resistance because the dose of dolutegravir in TRIUMEQ and TRIUMEQ PD is insufficient in these subpopulations. See the dolutegravir prescribing information. (1)

2 DOSAGE AND ADMINISTRATION

- Before initiating TRIUMEQ or TRIUMEQ PD, screen for the HLA‑B*5701 allele because TRIUMEQ and TRIUMEQ PD contain abacavir. (2.1).
- Prior to or when initiating TRIUMEQ or TRIUMEQ PD, test patients for HBV infection. (2.2)
- TRIUMEQ and TRIUMEQ PD may be taken with or without food. (2.4, 2.5)
- Adults: One tablet of TRIUMEQ daily. (2.4)

Pediatric Population Body Weight | Number of Tablets (once daily) | Recommended Daily Dose
 | TRIUMEQ PD Tablets (6 kg to <25 kg)
6 kg to <10 kg | 3 | 180 mg ABC, 15 mg DTG, and 90 mg 3TC
10 kg to <14 kg | 4 | 240 mg ABC, 20 mg DTG, and 120 mg 3TC
14 kg to <20 kg | 5 | 300 mg ABC, 25 mg DTG, and 150 mg 3TC
20 kg to <25 kg | 6 | 360 mg ABC, 30 mg DTG, and 180 mg 3TC
 | TRIUMEQ Tablets (≥25 kg)
≥25 kg | 1 | 600 mg ABC, 50 mg DTG, and 300 mg 3TC
ABC = abacavir, DTG = dolutegravir, 3TC = lamivudine.

- Do not substitute TRIUMEQ and TRIUMEQ PD on a milligram-per-milligram basis. (2.3)
- If dosing with certain UGT1A or CYP3A inducers, then the recommended dolutegravir dosage regimen should be adjusted. See Table 2 for complete dosing recommendations. (2.6)
- Because TRIUMEQ and TRIUMEQ PD are fixed-dose tablets and cannot be dose adjusted, TRIUMEQ and TRIUMEQ PD are not recommended in patients with creatinine clearance <30 mL/min and pediatric patients with a similar degree of renal impairment based on age-appropriate assessment of renal function, or patients with hepatic impairment. (2.7, 4)

3 DOSAGE FORMS AND STRENGTHS

- TRIUMEQ tablets: 600 mg of abacavir, 50 mg of dolutegravir, and 300 mg of lamivudine. (3)
- TRIUMEQ PD tablets for oral suspension: 60 mg of abacavir, 5 mg of dolutegravir, and 30 mg of lamivudine. (3)

4 CONTRAINDICATIONS

- Presence of HLA-B*5701 allele. (4)
- Prior hypersensitivity reaction to abacavir, dolutegravir, or lamivudine. (4)
- Coadministration with dofetilide. (4)
- Moderate or severe hepatic impairment. (4, 8.7)

5 WARNINGS AND PRECAUTIONS

- Hepatotoxicity has been reported in patients receiving a dolutegravir-containing regimen. Monitoring for hepatotoxicity is recommended. (5.3)
- Lactic acidosis and severe hepatomegaly with steatosis, including fatal cases, have been reported with the use of nucleoside analogues. (5.4)
- Immune reconstitution syndrome has been reported in patients treated with combination antiretroviral therapy. (5.6)
- TRIUMEQ tablets and TRIUMEQ PD tablets for oral suspension are not substitutable. (2.3, 5.7)

6 ADVERSE REACTIONS

The most commonly reported adverse reactions of at least moderate intensity and incidence at least 2% (in those receiving TRIUMEQ) were insomnia, headache, and fatigue. (6.1)

To report SUSPECTED ADVERSE REACTIONS, contact ViiV Healthcare at 1-877-844-8872 or FDA at 1-800-FDA-1088 or www.fda.gov/medwatch.

7 DRUG INTERACTIONS

Coadministration of TRIUMEQ or TRIUMEQ PD with other drugs can alter the concentration of other drugs and other drugs may alter the concentrations of TRIUMEQ or TRIUMEQ PD. The potential drug-drug interactions must be considered prior to and during therapy. (4, 7, 12.3)

8 USE IN SPECIFIC POPULATIONS

- Pediatrics: Not recommended for patients aged <3 months or weighing <6 kg. (8.4)
- TRIUMEQ and TRIUMEQ PD are not recommended in patients with creatinine clearance less than 30 mL/min and pediatric patients with a similar degree of renal impairment based on age-appropriate assessment of renal function. (8.6)
- If a dose reduction of abacavir, a component of TRIUMEQ and TRIUMEQ PD, is required for patients with mild hepatic impairment, then the individual components should be used. (8.7)

FULL PRESCRIBING INFORMATION

WARNING: HYPERSENSITIVITY REACTIONS, AND EXACERBATIONS OF HEPATITIS B

Hypersensitivity Reactions

Serious and sometimes fatal hypersensitivity reactions, with multiple organ involvement, have occurred with abacavir, a component of TRIUMEQ and TRIUMEQ PD (abacavir, dolutegravir, and lamivudine). Patients who carry the HLA‑B*5701 allele are at a higher risk of a hypersensitivity reaction to abacavir, although hypersensitivity reactions have occurred in patients who do not carry the HLA‑B*5701 allele [see Warnings and Precautions (5.1)].

TRIUMEQ and TRIUMEQ PD are contraindicated in patients with a prior hypersensitivity reaction to abacavir and in HLA‑B*5701-positive patients [see Contraindications (4), Warnings and Precautions (5.1)]. All patients should be screened for the HLA‑B*5701 allele prior to initiating therapy with TRIUMEQ or TRIUMEQ PD or reinitiation of therapy with TRIUMEQ or TRIUMEQ PD, unless patients have a previously documented HLA‑B*5701 allele assessment. Discontinue TRIUMEQ or TRIUMEQ PD immediately if a hypersensitivity reaction is suspected, regardless of HLA‑B*5701 status and even when other diagnoses are possible [see Contraindications (4), Warnings and Precautions (5.1)].

Following a hypersensitivity reaction to TRIUMEQ or TRIUMEQ PD, NEVER restart TRIUMEQ or TRIUMEQ PD or any other abacavir‑containing product because more severe symptoms, including death can occur within hours. Similar severe reactions have also occurred rarely following the reintroduction of abacavir-containing products in patients who have no history of abacavir hypersensitivity [see Warnings and Precautions (5.1)].

Exacerbations of Hepatitis B

All patients with HIV-1 should be tested for the presence of hepatitis B virus (HBV) prior to or when initiating TRIUMEQ or TRIUMEQ PD. Emergence of lamivudine-resistant HBV variants associated with lamivudine-containing antiretroviral regimens has been reported. If TRIUMEQ or TRIUMEQ PD is used in patients co-infected with HIV-1 and HBV, additional treatment should be considered for appropriate treatment of chronic HBV; otherwise, consider an alternative regimen.

Severe acute exacerbations of hepatitis B have been reported in patients who are co‑infected with HBV and HIV-1 and have discontinued lamivudine, a component of TRIUMEQ and TRIUMEQ PD. Closely monitor hepatic function in these patients and, if appropriate, initiate anti-HBV treatment [see Warnings and Precautions (5.2)].

1 INDICATIONS AND USAGE

TRIUMEQ and TRIUMEQ PD are indicated for the treatment of HIV-1 infection in adults and in pediatric patients aged at least 3 months and weighing at least 6 kg.

Limitations of Use:

TRIUMEQ and TRIUMEQ PD alone are not recommended in patients with resistance‑associated integrase substitutions or clinically suspected integrase strand transfer inhibitor (INSTI) resistance because the dose of dolutegravir in TRIUMEQ and TRIUMEQ PD is insufficient in these subpopulations. See full prescribing information for TIVICAY (dolutegravir).

2 DOSAGE AND ADMINISTRATION

2.1 Screening for HLA−B*5701 Allele prior to Initiating TRIUMEQ

Screen for the HLA‑B*5701 allele prior to initiating therapy with TRIUMEQ or TRIUMEQ PD [see Boxed Warning, Warnings and Precautions (5.1)].

2.2 Testing prior to or When Initiating Treatment with TRIUMEQ

Prior to or when initiating TRIUMEQ or TRIUMEQ PD, test patients for HBV infection [see Warnings and Precautions (5.2)].

2.3 Overview of TRIUMEQ Dosage Forms

TRIUMEQ is available in two dosage forms. Do not substitute TRIUMEQ tablets and TRIUMEQ PD tablets for oral suspension on a milligram-per-milligram basis due to differing pharmacokinetic profiles for the dolutegravir component [see Warnings and Precautions (5.7), Clinical Pharmacology (12.3)].

- TRIUMEQ tablets: 600 mg of abacavir, 50 mg of dolutegravir, and 300 mg of lamivudine. TRIUMEQ is recommended in adults and pediatric patients weighing at least 25 kg [see Dosage and Administration (2.4, 2.5)].
- TRIUMEQ PD tablets for oral suspension: 60 mg of abacavir, 5 mg of dolutegravir, and 30 mg of lamivudine. TRIUMEQ PD is recommended in pediatric patients weighing 6 kg to less than 25 kg [see Dosage and Administration (2.5)].
- Because TRIUMEQ PD is a fixed-dose tablet and the dosage of individual components cannot be adjusted, it may lead to a suboptimal dosing for patients weighing ≥25 kg. TRIUMEQ PD is not recommended in patients weighing 25 kg or more [see Dosage and Administration (2.4, 2.5)].

2.4 Recommended Dosage in Adults

TRIUMEQ is a fixed-dose combination product containing 600 mg of abacavir, 50 mg of dolutegravir, and 300 mg of lamivudine. The recommended dosage regimen of TRIUMEQ in adults is one tablet once daily orally with or without food. Do not use TRIUMEQ PD in adults.

2.5 Recommended Dosage and Administration Instructions for Pediatric Patients Weighing at Least 6 kg

The dosage and dosage form recommended for pediatric patients varies by weight as shown in Table 1 below.

Table 1. Recommended Dosage of TRIUMEQ Tablets and TRIUMEQ PD Tablets for Oral Suspension in Pediatric Patients
Body Weight | TRIUMEQ Tabletsa | TRIUMEQ PDb; Number of Tablets | Total Daily Dose
6 kg to <10 kg | Not recommended | 3 tablets once daily | 180 mg abacavir, 15 mg dolutegravir, and 90 mg lamivudine once daily
10 kg to <14 kg | Not recommended | 4 tablets once daily | 240 mg abacavir, 20 mg dolutegravir, and 120 mg lamivudine once daily
14 kg to <20 kg | Not recommended | 5 tablets once daily | 300 mg abacavir, 25 mg dolutegravir, and 150 mg lamivudine once daily
20 kg to <25 kg | Not recommended | 6 tablets once daily | 360 mg abacavir, 30 mg dolutegravir, and 180 mg lamivudine once daily
≥25 kg | 1 tablet once daily | Not recommended | 600 mg of abacavir, 50 mg of dolutegravir, and 300 mg of lamivudine
a TRIUMEQ is a fixed-dose combination product containing 600 mg of abacavir, 50 mg of dolutegravir, and 300 mg of lamivudine.
b TRIUMEQ PD is a fixed-dose combination product containing 60 mg of abacavir, 5 mg of dolutegravir, and 30 mg of lamivudine.

Administer TRIUMEQ PD tablets for oral suspension with or without food. Instruct patients (or instruct caregivers) to fully disperse the tablets for oral suspension in 20 mL of drinking water (if using 4, 5, or 6 tablets for oral suspension) or 15 mL (if using 3 tablets for oral suspension) in the supplied cup; swirl the suspension so that no lumps remain. After full dispersion, administer the oral suspension within 30 minutes of mixing [see Instructions for Use]. Do not swallow the tablets for oral suspension whole, and do not chew, cut, or crush the tablets.

For children unable to use the supplied cup, an appropriate-sized syringe may be used to administer the oral suspension.

Administer TRIUMEQ tablet with or without food. Do not chew, cut, or crush the tablet.

2.6 Dosage Recommendation with Certain Concomitant Medications

The dolutegravir dose in TRIUMEQ (50 mg) and TRIUMEQ PD (5 mg) is insufficient when coadministered with medications listed in Table 2 that may decrease dolutegravir concentrations; the following dolutegravir dosage regimen is recommended.

Table 2. Dosing Recommendations for TRIUMEQ and TRIUMEQ PD with Coadministered Medications
Coadministered Drug | Dosing Recommendation
Efavirenz, fosamprenavir/ritonavir, tipranavir/ritonavir, carbamazepine, or rifampin | In adults and in pediatric patients weighing at least 25 kg, the recommended dolutegravir dosage regimen is 50 mg twice daily. Thus, an additional TIVICAY 50-mg tablet, separated by 12 hours from TRIUMEQ, should be taken.; In pediatric patients weighing 6 kg to <25 kg, an additional weight-based dose of dolutegravir should be given separated by 12 hours from TRIUMEQ PD.; - 6 to <10 kg: administer an additional 15-mg dose of dolutegravir (3 TIVICAY PD tablets for oral suspension), 12 hours after TRIUMEQ PD. - 10 to <14 kg: administer an additional 20-mg dose of dolutegravir (4 TIVICAY PD tablets for oral suspension), 12 hours after TRIUMEQ PD. - 14 to <20 kg: administer an additional 25-mg dose of dolutegravir (5 TIVICAY PD tablets for oral suspension), 12 hours after TRIUMEQ PD. - 20 to <25 kg: administer an additional 30-mg dose of dolutegravir (6 TIVICAY PD tablets for oral suspension), 12 hours after TRIUMEQ PD.

2.7 Not Recommended Due to Lack of Dosage Adjustment

Because TRIUMEQ and TRIUMEQ PD are fixed-dose tablets and cannot be dose adjusted, TRIUMEQ and TRIUMEQ PD are not recommended in:

- patients with creatinine clearance <30 mL/min and pediatric patients with a similar degree of renal impairment based on age-appropriate renal function assessment. There are no data available on the use of lamivudine, a component of TRIUMEQ and TRIUMEQ PD, in pediatric patients with renal impairment [see Use in Specific Populations (8.4, 8.6)].
- patients with mild hepatic impairment. TRIUMEQ and TRIUMEQ PD are contraindicated in patients with moderate or severe hepatic impairment [see Contraindications (4), Use in Specific Populations (8.7)].

3 DOSAGE FORMS AND STRENGTHS

TRIUMEQ tablets are purple, biconvex, oval, and debossed with “572 Trı” on one side. Each film-coated tablet contains 600 mg of abacavir (as abacavir sulfate), 50 mg of dolutegravir (as dolutegravir sodium), and 300 mg of lamivudine [see Description (11)].

TRIUMEQ PD tablets for oral suspension are yellow, capsule-shaped, strawberry cream flavored, biconvex, film-coated tablets debossed with “SV WTU” on one side. Each film-coated tablet contains 60 mg of abacavir (as abacavir sulfate), 5 mg of dolutegravir (as dolutegravir sodium), and 30 mg of lamivudine [see Description (11)].

4 CONTRAINDICATIONS

TRIUMEQ and TRIUMEQ PD are contraindicated in patients:

- who have the HLA-B*5701 allele [see Warnings and Precautions (5.1)].
- with prior hypersensitivity reaction to abacavir, dolutegravir [see Warnings and Precautions (5.1)], or lamivudine.
- receiving dofetilide due to the potential for increased dofetilide plasma concentrations and the risk for serious and/or life-threatening events with concomitant use of dolutegravir [see Drug Interactions (7)].
- with moderate or severe hepatic impairment [see Use in Specific Populations (8.7)].

5 WARNINGS AND PRECAUTIONS

5.1 Hypersensitivity Reactions

Hypersensitivity reactions have been reported with the use of abacavir or dolutegravir, components of TRIUMEQ and TRIUMEQ PD.

Abacavir

Serious and sometimes fatal hypersensitivity reactions have occurred with abacavir-containing regimens. See full prescribing information for ZIAGEN (abacavir).

Abacavir hypersensitivity reactions have included multi-organ failure and anaphylaxis and typically occurred within the first 6 weeks of treatment with abacavir (median time to onset was 9 days); although abacavir hypersensitivity reactions have occurred any time during treatment [see Adverse Reactions (6.1)]. Patients who carry the HLA‑B*5701 allele are at a higher risk of abacavir hypersensitivity reactions; although, patients who do not carry the HLA‑B*5701 allele have developed hypersensitivity reactions. Hypersensitivity to abacavir was reported in approximately 206 (8%) of 2,670 patients in 9 clinical trials with abacavir-containing products where HLA‑B*5701 screening was not performed. The incidence of suspected abacavir hypersensitivity reactions in clinical trials was 1% when subjects carrying the HLA-B*5701 allele were excluded. In any patient treated with abacavir, the clinical diagnosis of hypersensitivity reaction must remain the basis of clinical decision making.

Due to the potential for severe, serious, and possibly fatal hypersensitivity reactions with abacavir:

- All patients should be screened for the HLA‑B*5701 allele prior to initiating therapy with TRIUMEQ or TRIUMEQ PD or reinitiation of therapy with TRIUMEQ or TRIUMEQ PD, unless patients have a previously documented HLA‑B*5701 allele assessment.
- TRIUMEQ and TRIUMEQ PD are contraindicated in patients with a prior hypersensitivity reaction to abacavir and in HLA‑B*5701‑positive patients.
- Before starting TRIUMEQ or TRIUMEQ PD, review medical history for prior exposure to any abacavir-containing product. NEVER restart TRIUMEQ or TRIUMEQ PD or any other abacavir-containing product following a hypersensitivity reaction to abacavir, regardless of HLA‑B*5701 status.
- To reduce the risk of a life‑threatening hypersensitivity reaction, regardless of HLA‑B*5701 status, discontinue TRIUMEQ or TRIUMEQ PD immediately if a hypersensitivity reaction is suspected, even when other diagnoses are possible (e.g., acute onset respiratory diseases such as pneumonia, bronchitis, pharyngitis, or influenza; gastroenteritis; or reactions to other medications). Clinical status, including liver chemistries, should be monitored and appropriate therapy initiated.
- If a hypersensitivity reaction cannot be ruled out, do not restart TRIUMEQ or TRIUMEQ PD or any other abacavir-containing products because more severe symptoms, which may include life-threatening hypotension and death, can occur within hours.
- Clinically, it is not possible to determine whether a hypersensitivity reaction with TRIUMEQ or TRIUMEQ PD would be caused by abacavir or dolutegravir. Therefore, never restart TRIUMEQ or TRIUMEQ PD or any other abacavir- or dolutegravir-containing product in patients who have stopped therapy with TRIUMEQ or TRIUMEQ PD due to a hypersensitivity reaction.
- If a hypersensitivity reaction is ruled out, patients may restart TRIUMEQ or TRIUMEQ PD. Rarely, patients who have stopped abacavir for reasons other than symptoms of hypersensitivity have also experienced life-threatening reactions within hours of reinitiating abacavir therapy. Therefore, reintroduction of TRIUMEQ or TRIUMEQ PD, or any other abacavir-containing product, is recommended only if medical care can be readily accessed.
- A Medication Guide and Warning Card that provide information about recognition of abacavir hypersensitivity reactions should be dispensed with each new prescription and refill.

Dolutegravir

Hypersensitivity reactions have been reported and were characterized by rash, constitutional findings, and sometimes organ dysfunction, including liver injury. The events were reported in <1% of subjects receiving TIVICAY in Phase 3 clinical trials. Discontinue TRIUMEQ or TRIUMEQ PD and other suspect agents immediately if signs or symptoms of hypersensitivity reactions develop (including, but not limited to, severe rash or rash accompanied by fever, general malaise, fatigue, muscle or joint aches, blisters or peeling of the skin, oral blisters or lesions, conjunctivitis, facial edema, hepatitis, eosinophilia, angioedema, difficulty breathing). Clinical status, including liver aminotransferases, should be monitored and appropriate therapy initiated. Delay in stopping treatment with TRIUMEQ or TRIUMEQ PD or other suspect agents after the onset of hypersensitivity may result in a life-threatening reaction.

Clinically, it is not possible to determine whether a hypersensitivity reaction with TRIUMEQ or TRIUMEQ PD would be caused by abacavir or dolutegravir. Therefore, never restart TRIUMEQ or TRIUMEQ PD or any other abacavir- or dolutegravir-containing product in patients who have stopped therapy with TRIUMEQ or TRIUMEQ PD due to a hypersensitivity reaction.

5.2 Patients Co-infected with HIV-1 and HBV: Emergence of Lamivudine-Resistant HBV and the Risk of Posttreatment Exacerbations of HBV

All patients with HIV-1 should be tested for the presence of HBV prior to or when initiating TRIUMEQ or TRIUMEQ PD.

Emergence of Lamivudine Resistant HBV

Safety and efficacy of lamivudine have not been established for treatment of chronic HBV in subjects dually infected with HIV-1 and HBV. Emergence of HBV variants associated with resistance to lamivudine has been reported in HIV‑1−infected subjects who have received lamivudine‑containing antiretroviral regimens in the presence of concurrent infection with HBV. If a decision is made to administer TRIUMEQ or TRIUMEQ PD to patients co-infected with HIV-1 and HBV, additional treatment should be considered for appropriate treatment of chronic HBV; otherwise, consider an alternative regimen.

Severe Acute Exacerbations of HBV in Patients Co-infected with HIV-1 and HBV

Severe acute exacerbations of HBV have been reported in patients who are co-infected with HIV-1 and HBV and have discontinued products containing lamivudine, and may occur with discontinuation of TRIUMEQ or TRIUMEQ PD. Patients who are co-infected with HIV-1 and HBV who discontinue TRIUMEQ or TRIUMEQ PD should be closely monitored with both clinical and laboratory follow-up for at least several months after stopping treatment with TRIUMEQ or TRIUMEQ PD. If appropriate, initiation of anti-HBV therapy may be warranted, especially in patients with advanced liver disease or cirrhosis since posttreatment exacerbation of hepatitis may lead to hepatic decompensation and liver failure.

5.3 Hepatotoxicity

Hepatic adverse events have been reported in patients receiving a dolutegravir-containing regimen [see Adverse Reactions (6.1, 6.2)]. Patients with underlying hepatitis B or C may be at increased risk for worsening or development of transaminase elevations with use of TRIUMEQ or TRIUMEQ PD [see Adverse Reactions (6.1)]. In some cases, the elevations in transaminases were consistent with immune reconstitution syndrome or hepatitis B reactivation particularly in the setting where anti-hepatitis therapy was withdrawn. Cases of hepatic toxicity, including elevated serum liver biochemistries, hepatitis, and acute liver failure, have also been reported in patients, including pediatric patients receiving a dolutegravir-containing regimen who had no pre-existing hepatic disease or other identifiable risk factors. Drug-induced liver injury leading to liver transplant has been reported with TRIUMEQ. Monitoring for hepatotoxicity is recommended.

5.4 Lactic Acidosis and Severe Hepatomegaly with Steatosis

Lactic acidosis and severe hepatomegaly with steatosis, including fatal cases, have been reported with the use of nucleoside analogues, including abacavir and lamivudine (components of TRIUMEQ and TRIUMEQ PD). A majority of these cases have been in women. Female sex and obesity may be risk factors for the development of lactic acidosis and severe hepatomegaly with steatosis in patients treated with antiretroviral nucleoside analogues. See full prescribing information for ZIAGEN (abacavir) and EPIVIR (lamivudine). Treatment with TRIUMEQ or TRIUMEQ PD should be suspended in any patient who develops clinical or laboratory findings suggestive of lactic acidosis or pronounced hepatotoxicity, which may include hepatomegaly and steatosis even in the absence of marked transaminase elevations.

5.5 Risk of Adverse Reactions or Loss of Virologic Response Due to Drug Interactions

The concomitant use of TRIUMEQ or TRIUMEQ PD and other drugs may result in known or potentially significant drug interactions, some of which may lead to [see Contraindications (4), Drug Interactions (7.3)]:

- Loss of therapeutic effect of TRIUMEQ or TRIUMEQ PD and possible development of resistance.
- Possible clinically significant adverse reactions from greater exposures of concomitant drugs.

See Table 6 for steps to prevent or manage these possible and known significant drug interactions, including dosing recommendations. Consider the potential for drug interactions prior to and during therapy with TRIUMEQ or TRIUMEQ PD, review concomitant medications during therapy with TRIUMEQ or TRIUMEQ PD, and monitor for the adverse reactions associated with the concomitant drugs.

5.6 Immune Reconstitution Syndrome

Immune reconstitution syndrome has been reported in patients treated with combination antiretroviral therapy, including TRIUMEQ or TRIUMEQ PD. During the initial phase of combination antiretroviral treatment, patients whose immune systems respond may develop an inflammatory response to indolent or residual opportunistic infections (such as Mycobacterium avium infection, cytomegalovirus, Pneumocystis jirovecii pneumonia [PCP], or tuberculosis), which may necessitate further evaluation and treatment.

Autoimmune disorders (such as Graves’ disease, polymyositis, Guillain-Barré syndrome, autoimmune hepatitis) have also been reported to occur in the setting of immune reconstitution; however, the time to onset is more variable, and can occur many months after initiation of treatment.

5.7 Different Formulations Are Not Substitutable

TRIUMEQ and TRIUMEQ PD are not bioequivalent and are not substitutable on a milligram-per-milligram basis [see Clinical Pharmacology (12.3)]. If a pediatric patient switches from the tablets for oral suspension to the tablets, the dosage must be adjusted [see Dosage and Administration (2.3, 2.5)]. Incorrect dosing of a given formulation may result in underdosing and loss of therapeutic effect and possible development of resistance or possible clinically significant adverse reactions from greater exposure to the individual components.

5.8 Myocardial Infarction

Several prospective, observational, epidemiological studies have reported an association with the use of abacavir and the risk of myocardial infarction (MI). Meta-analyses of randomized, controlled clinical trials have observed no excess risk of MI in abacavir‑treated subjects as compared with control subjects. To date, there is no established biological mechanism to explain a potential increase in risk. In totality, the available data from the observational studies and from controlled clinical trials show inconsistency; therefore, evidence for a causal relationship between abacavir and the risk of MI is inconclusive.

As a precaution, the underlying risk of coronary heart disease should be considered when prescribing antiretroviral therapies, including abacavir, and action taken to minimize all modifiable risk factors (e.g., hypertension, hyperlipidemia, diabetes mellitus, smoking).

6 ADVERSE REACTIONS

The following adverse reactions are discussed in other sections of the labeling:

- Serious and sometimes fatal hypersensitivity reaction [see Boxed Warning, Warnings and Precautions (5.1)].
- Exacerbations of hepatitis B [see Boxed Warning, Warnings and Precautions (5.3)].
- Hepatotoxicity [see Warnings and Precautions (5.3)].
- Lactic acidosis and severe hepatomegaly with steatosis [see Warnings and Precautions (5.4)].
- Immune reconstitution syndrome [see Warnings and Precautions (5.6)].
- Myocardial infarction [see Warnings and Precautions (5.8)].

6.1 Clinical Trials Experience

Because clinical trials are conducted under widely varying conditions, adverse reaction rates observed in the clinical trials of a drug cannot be directly compared with rates in the clinical trials of another drug and may not reflect the rates observed in clinical practice.

Clinical Trials in Adults

Serious and Fatal Abacavir-Associated Hypersensitivity Reactions: In clinical trials, serious and sometimes fatal hypersensitivity reactions have occurred with abacavir, a component of TRIUMEQ and TRIUMEQ PD [see Boxed Warning, Warnings and Precautions (5.1)]. These reactions have been characterized by 2 or more of the following signs or symptoms: (1) fever; (2) rash; (3) gastrointestinal symptoms (including nausea, vomiting, diarrhea, or abdominal pain); (4) constitutional symptoms (including generalized malaise, fatigue, or achiness); (5) respiratory symptoms (including dyspnea, cough, or pharyngitis). Almost all abacavir hypersensitivity reactions include fever and/or rash as part of the syndrome.

Other signs and symptoms have included lethargy, headache, myalgia, edema, arthralgia, and paresthesia. Anaphylaxis, liver failure, renal failure, hypotension, adult respiratory distress syndrome, respiratory failure, myolysis, and death have occurred in association with these hypersensitivity reactions. Physical findings have included lymphadenopathy, mucous membrane lesions (conjunctivitis and mouth ulcerations), and maculopapular or urticarial rash (although some patients had other types of rashes and others did not have a rash). There were reports of erythema multiforme. Laboratory abnormalities included elevated liver chemistries, elevated creatine phosphokinase, elevated creatinine, and lymphopenia and abnormal chest x‑ray findings (predominantly infiltrates, which were localized).

Serious Dolutegravir Hypersensitivity Reactions: In clinical trials, hypersensitivity reactions have occurred with dolutegravir, a component of TRIUMEQ and TRIUMEQ PD [see Warnings and Precautions (5.1)]. These hypersensitivity reactions have been characterized by rash, constitutional findings, and sometimes organ dysfunction, including liver injury.

Additional Treatment-Emergent Adverse Drug Reactions (ADRs) with Use of TRIUMEQ: The safety assessment of TRIUMEQ is primarily based on the analyses of data from a randomized, international, multicenter, double-blind, active-controlled trial, SINGLE (ING114467) and supported by data in treatment-experienced, INSTI-naive subjects from SAILING (ING111762) and by data from other treatment-naive trials. See full prescribing information for TIVICAY.

Treatment-Naive Subjects: In SINGLE, 833 adult subjects were randomized and received at least one dose of either dolutegravir (TIVICAY) 50 mg with fixed-dose abacavir and lamivudine (EPZICOM) once daily (n = 414) or fixed-dose efavirenz/emtricitabine/tenofovir (ATRIPLA) once daily (n = 419) (study treatment was blinded through Week 96 and open-label from Week 96 through Week 144). Through 144 weeks, the rate of adverse events leading to discontinuation was 4% in subjects receiving TIVICAY + EPZICOM and 14% in subjects receiving ATRIPLA once daily.

Treatment‑emergent ADRs of moderate to severe intensity observed in at least 2% of subjects in either treatment arm of SINGLE are provided in Table 3.

Table 3. Treatment-Emergent Adverse Drug Reactions of at Least Moderate Intensity (Grades 2 to 4) and at Least 2% Frequency in Treatment-Naive Subjects in SINGLE (Week 144 Analysis)
Adverse Reaction | TIVICAY + EPZICOM; Once Daily; (n = 414) | ATRIPLA; Once Daily; (n = 419)
Psychiatric
Insomnia | 3% | 3%
Depression | 1% | 2%
Abnormal dreams | <1% | 2%
Nervous System
Dizziness | <1% | 5%
Headache | 2% | 2%
Gastrointestinal
Nausea | <1% | 3%
Diarrhea | <1% | 2%
General Disorders
Fatigue | 2% | 2%
Skin and Subcutaneous Tissue
Rasha | <1% | 6%
Ear and Labyrinth
Vertigo | 0 | 2%
a Includes pooled terms: rash, rash generalized, rash macular, rash maculo-papular, rash pruritic, and drug eruption.

Treatment-Experienced Subjects: SAILING is an international, double-blind trial in INSTI-naive, antiretroviral treatment-experienced adult subjects. Subjects were randomized and received either TIVICAY 50 mg once daily or raltegravir 400 mg twice daily with investigator-selected background regimen consisting of up to 2 agents, including at least one fully active agent. At 48 weeks, the rate of adverse events leading to discontinuation was consistent with that seen in the overall treatment-naive patient population. See full prescribing information for TIVICAY.

The ADRs observed in the subset of subjects who received TIVICAY + EPZICOM were generally consistent with those seen in the overall treatment-naive patient population.

Less Common Adverse Reactions Observed in Clinical Trials: The following adverse reactions occurred in <2% of treatment-naive or treatment-experienced subjects in any one trial. These events have been included because of their seriousness and/or assessment of potential causal relationship.

Gastrointestinal Disorders: Abdominal pain, abdominal distention, abdominal discomfort, dyspepsia, flatulence, gastroesophageal reflux disease, upper abdominal pain, vomiting.

General Disorders: Fever, lethargy.

Hepatobiliary Disorders: Hepatitis.

Metabolism and Nutrition Disorders: Anorexia, hypertriglyceridemia.

Musculoskeletal Disorders: Arthralgia, myositis.

Nervous System Disorders: Somnolence.

Psychiatric Disorders: Suicidal ideation, attempt, behavior, or completion. These events were observed primarily in subjects with a pre-existing history of depression or other psychiatric illness. Nightmare and sleep disorder.

Renal and Urinary Disorders: Renal impairment.

Skin and Subcutaneous Tissue Disorders: Pruritus.

Laboratory Abnormalities: Treatment-Naive Subjects: Selected laboratory abnormalities (Grades 2 to 4) with a worsening grade from baseline and representing the worst-grade toxicity in at least 2% of subjects in SINGLE are presented in Table 4. The mean change from baseline observed for selected lipid values is presented in Table 5.

Table 4. Selected Laboratory Abnormalities (Grades 2 to 4) in Treatment-Naive Subjects in SINGLE (Week 144 Analysis)
Laboratory Abnormality | TIVICAY + EPZICOM Once Daily; (n = 414) | ATRIPLA; Once Daily; (n = 419)
ALT
Grade 2 (>2.5-5.0 x ULN) | 3% | 5%
Grade 3 to 4 (>5.0 x ULN) | 1% | <1%
AST
Grade 2 (>2.5-5.0 x ULN) | 3% | 4%
Grade 3 to 4 (>5.0 x ULN) | 1% | 3%
Creatine kinase
Grade 2 (6.0-9.9 x ULN) | 5% | 3%
Grade 3 to 4 (≥10.0 x ULN) | 7% | 8%
Hyperglycemia
Grade 2 (126-250 mg/dL) | 9% | 6%
Grade 3 (>250 mg/dL) | 2% | <1%
Lipase
Grade 2 (>1.5-3.0 x ULN) | 11% | 11%
Grade 3 to 4 (>3.0 ULN) | 5% | 4%
Total neutrophils
Grade 2 (0.75-0.99 x 10^9) | 4% | 5%
Grade 3 to 4 (<0.75 x 10^9) | 3% | 3%
ALT = Alanine aminotransferase, AST = Aspartate aminotransferase, ULN = upper limit of normal.

Table 5. Mean Change from Baseline in Fasted Lipid Values in Treatment-Naive Subjects in SINGLE (Week 144 Analysisa)
Lipid | TIVICAY + EPZICOM Once Daily; (n = 414) | ATRIPLA; Once Daily; (n = 419)
Cholesterol (mg/dL) | 24.0 | 26.7
HDL cholesterol (mg/dL) | 5.4 | 7.2
LDL cholesterol (mg/dL) | 16.0 | 14.6
Triglycerides (mg/dL) | 13.6 | 31.9
HDL = High-density lipoprotein, LDL = Low-density lipoprotein.
a Subjects on lipid-lowering agents at baseline were excluded from these analyses (TIVICAY + EPZICOM: n = 30 and ATRIPLA: n = 27). Seventy-two subjects initiated a lipid-lowering agent post-baseline; their last fasted on-treatment values (prior to starting the agent) were used regardless of whether they discontinued the agent (TIVICAY + EPZICOM: n = 36 and ATRIPLA: n = 36).

Treatment-Experienced Subjects: Laboratory abnormalities observed in SAILING were generally similar compared with observations seen in the treatment-naive trials.

Hepatitis C Virus Co-infection: In SINGLE, the pivotal Phase 3 trial, subjects with hepatitis C virus co-infection were permitted to enroll provided that baseline liver chemistry tests did not exceed 5 times the upper limit of normal; subjects with hepatitis B co-infection were excluded. Overall, the safety profile in subjects with hepatitis C virus co-infection was similar to that observed in subjects without hepatitis C co-infection, although the rates of aspartate aminotransferase (AST) and alanine aminotransferase (ALT) abnormalities were higher in the subgroup with hepatitis C virus co-infection for both treatment groups. Grades 2 to 4 ALT abnormalities in hepatitis C co-infected compared with HIV mono-infected subjects receiving TRIUMEQ were observed in 15% and 2% (vs. 24% and 4% of subjects treated with ATRIPLA) (Week 96 analysis), respectively [see Warnings and Precautions (5.2)]. See also full prescribing information for TIVICAY.

Changes in Serum Creatinine: Dolutegravir has been shown to increase serum creatinine due to inhibition of tubular secretion of creatinine without affecting renal glomerular function [see Clinical Pharmacology (12.2)]. Increases in serum creatinine occurred within the first 4 weeks of treatment and remained stable through 144 weeks. In SINGLE, a mean change from baseline of 0.14 mg/dL (range: -0.25 mg/dL to 0.81 mg/dL) was observed after 144 weeks of treatment. Creatinine increases were similar in treatment-experienced subjects.

Abacavir and Lamivudine: Laboratory abnormalities observed in clinical trials of ZIAGEN (in combination with other antiretroviral treatment) were anemia, neutropenia, liver function test abnormalities, and elevations of creatine phosphokinase (CPK), blood glucose, and triglycerides. Additional laboratory abnormalities observed in clinical trials of EPIVIR (in combination with other antiretroviral treatment) were thrombocytopenia and elevated levels of bilirubin, amylase, and lipase.

Clinical Trials Experience in Pediatric Subjects

Abacavir, Dolutegravir and Lamivudine: The safety of TRIUMEQ PD and TRIUMEQ in pediatric subjects with HIV-1 infection weighing at least 6 kg was evaluated in the IMPAACT 2019 trial. This was a multicenter, open-label, non-comparative trial of pediatric subjects with HIV-1 infection, younger than 12 years of age. Fifty-seven subjects weighing at least 6 kg to less than 40 kg were enrolled in this trial [see Use in Specific Populations (8.4), Clinical Pharmacology (12.3), Clinical Studies (14.2)]. Overall, the safety data in this pediatric study was similar to that seen in adults.

The safety analysis through Week 48 included 57 subjects weighing at least 6 kg at enrollment who received the recommended dose (determined by weight) and formulation. This analysis showed that 26% of subjects experienced clinical adverse reactions. The most common adverse reactions were classified as laboratory abnormalities and included decreased glomerular filtration rate (n = 13, 23%), increased blood creatinine (n = 10, 18%), and increased ALT (n = 3, 5%). All other adverse reactions occurred at a rate of <2% of participants. Two subjects reported Grade 3 or 4 adverse reactions. One subject, an 8-year-old female who weighed 22 kg at baseline, experienced Grade 3 increased blood creatinine and Grade 3 decreased glomerular filtration rate. By Week 48, the glomerular filtration rate was improving, and the events did not lead to drug discontinuation. Another subject, a 7-year-old male who weighed 20 kg at baseline, experienced drug-induced liver injury with Grade 4 increased ALT and AST following 36 weeks of treatment with TRIUMEQ PD. Clinical signs or symptoms of hepatitis were not reported, and ALT and AST values normalized after TRIUMEQ PD was discontinued.

Abacavir and Lamivudine: The safety of once-daily compared with twice-daily dosing of abacavir and lamivudine, administered as either single products or as EPZICOM, was assessed in the ARROW trial (n = 336). Primary safety assessment in the ARROW (COL105677) trial was based on Grade 3 and Grade 4 adverse events. One event of Grade 4 hepatitis in the once-daily cohort was considered as uncertain causality by the investigator and all other Grade 3 or 4 adverse events were considered not related by the investigator. No additional safety issues were identified in pediatric subjects compared with historical data in adults.

Dolutegravir: The safety of dolutegravir in pediatric subjects with HIV-1 infection weighing at least 6 kg was evaluated in the IMPAACT P1093 trial [see Use in Specific Populations (8.4), Clinical Pharmacology (12.3)]. Overall, the safety data in this pediatric study was similar to that seen in adults.

IMPAACT P1093 is an ongoing multicenter, open-label, non-comparative trial of pediatric subjects with HIV-1 infection, aged <18 years. One hundred and forty-two subjects weighing at least 6 kg were enrolled in this trial [see Use in Specific Populations (8.4), Clinical Pharmacology (12.3), Clinical Studies (14.2)].

The safety analysis through Week 24 included 60 subjects weighing at least 6 kg at enrollment who received the recommended dose (determined by weight and age) and formulation. This analysis showed that 13% of subjects experienced adverse reactions. Grade 1 to 2 adverse reactions reported by more than one subject was immune reconstitution inflammatory syndrome (n = 2). There were no Grade 3 or 4 adverse reactions reported. No adverse reactions led to discontinuation.

The Grade 3 or 4 laboratory abnormalities reported in more than one subject weighing at least 6 kg at enrollment were decreased neutrophil count (n = 5), decreased blood bicarbonate (n = 3), increased lipase (n = 2), and increased blood potassium (n = 2). These laboratory events were not considered to be drug related. Changes in median serum creatinine were similar to those observed in adults.

6.2 Postmarketing Experience

In addition to adverse reactions reported from clinical trials, the following adverse reactions have been identified during postmarketing use with one or more of the components of TRIUMEQ and TRIUMEQ PD. Because these reactions are reported voluntarily from a population of uncertain size, it is not always possible to reliably estimate their frequency or establish a causal relationship to drug exposure.

Blood and Lymphatic Systems

Aplastic anemia, anemia (including pure red cell aplasia, sideroblastic anemia and severe anemias progressing on therapy), lymphadenopathy, splenomegaly.

Digestive

Stomatitis.

Gastrointestinal

Pancreatitis.

General

Weakness.

Hepatobiliary Disorders

Acute liver failure, liver transplant [see Warnings and Precautions (5.3)].

Hypersensitivity

Sensitization reactions (including anaphylaxis), urticaria [see Warnings and Precautions (5.1), Adverse Reactions (6.1)].

Investigations

Weight increased.

Metabolism and Nutrition Disorders

Hyperlactemia.

Musculoskeletal

CPK elevation, muscle weakness, myalgia, rhabdomyolysis.

Nervous

Paresthesia, peripheral neuropathy, seizures.

Psychiatric

Anxiety.

Respiratory

Abnormal breath sounds/wheezing.

Skin

Alopecia, erythema multiforme. Suspected Stevens‑Johnson syndrome (SJS) and toxic epidermal necrolysis (TEN) have been reported in patients receiving abacavir primarily in combination with medications known to be associated with SJS and TEN, respectively. Because of the overlap of clinical signs and symptoms between hypersensitivity to abacavir and SJS and TEN, and the possibility of multiple drug sensitivities in some patients, abacavir should be discontinued and not restarted in such cases [see Adverse Reactions (6.1)].

7 DRUG INTERACTIONS

7.1 Effect of Dolutegravir on the Pharmacokinetics of Other Agents

In vitro, dolutegravir inhibited the renal organic cation transporters (OCT)2 (IC50 = 1.93 microM) and multidrug and toxin extrusion transporter (MATE)1 (IC50 = 6.34 microM). In vivo, dolutegravir inhibits tubular secretion of creatinine by inhibiting OCT2 and potentially MATE1. Dolutegravir may increase plasma concentrations of drugs eliminated via OCT2 or MATE1 (dofetilide, dalfampridine, and metformin) [see Contraindications (4), Drug Interactions (7.3)].

In vitro, dolutegravir inhibited the basolateral renal transporters, organic anion transporter (OAT) 1 (IC50 = 2.12 microM) and OAT3 (IC50 = 1.97 microM). However, in vivo, dolutegravir did not alter the plasma concentrations of tenofovir or para-amino hippurate, substrates of OAT1 and OAT3.

In vitro, dolutegravir did not inhibit (IC50 >50 microM) the following: cytochrome P450 (CYP)1A2, CYP2A6, CYP2B6, CYP2C8, CYP2C9, CYP2C19, CYP2D6, CYP3A, uridine diphosphate (UDP)-glucuronosyl transferase (UGT)1A1, UGT2B7, P-glycoprotein (P-gp), breast cancer resistance protein (BCRP), bile salt export pump (BSEP), organic anion transporter polypeptide (OATP)1B1, OATP1B3, OCT1, or multidrug resistance protein (MRP)2, or MRP4. In vitro, dolutegravir did not induce CYP1A2, CYP2B6, CYP3A4. Based on these data and the results of drug interaction trials, dolutegravir is not expected to affect the pharmacokinetics of drugs that are substrates of these enzymes or transporters.

In drug interaction trials, dolutegravir did not have a clinically relevant effect on the pharmacokinetics of the following drugs: tenofovir, methadone, midazolam, rilpivirine, and oral contraceptives containing norgestimate and ethinyl estradiol. Using cross-study comparisons to historical pharmacokinetic data for each interacting drug, dolutegravir did not appear to affect the pharmacokinetics of the following drugs: atazanavir, darunavir, efavirenz, etravirine, fosamprenavir, lopinavir, ritonavir, and boceprevir.

7.2 Effect of Other Agents on the Pharmacokinetics of Dolutegravir

Dolutegravir is metabolized by UGT1A1 with some contribution from CYP3A. Dolutegravir is also a substrate of UGT1A3, UGT1A9, BCRP, and P-gp in vitro. Drugs that induce those enzymes and transporters may decrease dolutegravir plasma concentrations and reduce the therapeutic effect of dolutegravir.

Coadministration of dolutegravir and other drugs that inhibit these enzymes may increase dolutegravir plasma concentrations.

Etravirine significantly reduced plasma concentrations of dolutegravir, but the effect of etravirine was mitigated by coadministration of lopinavir/ritonavir or darunavir/ritonavir and is expected to be mitigated by atazanavir/ritonavir (Table 6) [see Drug Interactions (7.3), Clinical Pharmacology (12.3)].

In vitro, dolutegravir was not a substrate of OATP1B1 or OATP1B3.

Darunavir/ritonavir, lopinavir/ritonavir, rilpivirine, tenofovir, boceprevir, prednisone, rifabutin, and omeprazole had no clinically significant effect on the pharmacokinetics of dolutegravir.

7.3 Established and Other Potentially Significant Drug Interactions

There were no drug-drug interaction trials conducted with the abacavir, dolutegravir, and lamivudine fixed-dose combination tablets.

Information regarding potential drug interactions with the individual components of TRIUMEQ and TRIUMEQ PD are provided below. These recommendations are based on either drug interaction trials or predicted interactions due to the expected magnitude of interaction and potential for serious adverse events or loss of efficacy. [See Contraindications (4), Clinical Pharmacology (12.3).]

Table 6. Established and Other Potentially Significant Drug Interactions for Dolutegravir: Alterations in Dose May Be Recommended Based on Drug Interaction Trials or Predicted Interactions
Concomitant Drug Class: Drug Name | Effect on Concentration | Clinical Comment
HIV-1 Antiviral Agents
Non-nucleoside reverse transcriptase inhibitor:; Etravirinea | ↓Dolutegravir | Use of TRIUMEQ or TRIUMEQ PD with etravirine without coadministration of atazanavir/ritonavir, darunavir/ritonavir, or lopinavir/ritonavir is not recommended.
Non-nucleoside reverse transcriptase inhibitor:; Efavirenza | ↓Dolutegravir | In adults and in pediatric patients weighing at least 25 kg, adjust dolutegravir dose to 50 mg twice daily. An additional 50-mg dose of TIVICAY should be taken, separated by 12 hours from TRIUMEQ.; In pediatric patients weighing 6 to <25 kg, an additional weight-based dose of dolutegravir should be given separated by 12 hours from TRIUMEQ PD.; - 6 to <10 kg: administer an additional 15-mg dose of dolutegravir (3 TIVICAY PD tablets for oral suspension), 12 hours after TRIUMEQ PD. - 10 to <14 kg: administer an additional 20-mg dose of dolutegravir (4 TIVICAY PD tablets for oral suspension), 12 hours after TRIUMEQ PD. - 14 to <20 kg: administer an additional 25-mg dose of dolutegravir (5 TIVICAY PD tablets for oral suspension), 12 hours after TRIUMEQ PD. - 20 to <25 kg: administer an additional 30-mg dose of dolutegravir (6 TIVICAY PD tablets for oral suspension), 12 hours after TRIUMEQ PD.
Non-nucleoside reverse transcriptase inhibitor:; Nevirapine | ↓Dolutegravir | Avoid coadministration with TRIUMEQ or TRIUMEQ PD because there are insufficient data to make dosing recommendations.
Protease inhibitor:; Fosamprenavir/ritonavira Tipranavir/ritonavira | ↓Dolutegravir | In adults and in pediatric patients weighing at least 25 kg, adjust dolutegravir dose to 50 mg twice daily. An additional TIVICAY 50-mg dose should be taken, separated by 12 hours from TRIUMEQ.; In pediatric patients weighing 10 to <25 kg, an additional weight-based dose of dolutegravir should be given separated by 12 hours from TRIUMEQ PD.; - 6 to <10 kg: administer an additional 15-mg dose of dolutegravir (3 TIVICAY PD tablets for oral suspension), 12 hours after TRIUMEQ PD. - 10 to <14 kg: administer an additional 20-mg dose of dolutegravir (4 TIVICAY PD tablets for oral suspension), 12 hours after TRIUMEQ PD. - 14 to <20 kg: administer an additional 25-mg dose of dolutegravir (5 TIVICAY PD tablets for oral suspension), 12 hours after TRIUMEQ PD. - 20 to <25 kg: administer an additional 30-mg dose of dolutegravir (6 TIVICAY PD tablets for oral suspension), 12 hours after TRIUMEQ PD.
Other Agents
Antiarrhythmic:; Dofetilide | ↑Dofetilide | Coadministration is contraindicated with TRIUMEQ and TRIUMEQ PD [see Contraindications (4)].
Potassium channel blocker:; Dalfampridine | ↑Dalfampridine | Elevated levels of dalfampridine increase the risk of seizures. The potential benefits of taking dalfampridine concurrently with TRIUMEQ or TRIUMEQ PD should be considered against the risk of seizures in these patients.
Carbamazepinea | ↓Dolutegravir | In adults and in pediatric patients weighing at least 25 kg, adjust dolutegravir dose to 50 mg twice daily. An additional TIVICAY 50-mg dose should be taken, separated by 12 hours from TRIUMEQ.; In pediatric patients weighing 6 to <25 kg, an additional weight-based dose of dolutegravir should be given separated by 12 hours from TRIUMEQ PD.; - 6 to <10 kg: administer an additional 15-mg dose of dolutegravir (3 TIVICAY PD tablets for oral suspension), 12 hours after TRIUMEQ PD. - 10 to <14 kg: administer an additional 20-mg dose of dolutegravir (4 TIVICAY PD tablets for oral suspension), 12 hours after TRIUMEQ PD. - 14 to <20 kg: administer an additional 25-mg dose of dolutegravir (5 TIVICAY PD tablets for oral suspension), 12 hours after TRIUMEQ PD. - 20 to <25 kg: administer an additional 30-mg dose of dolutegravir (6 TIVICAY PD tablets for oral suspension), 12 hours after TRIUMEQ PD.
Oxcarbazepine Phenytoin Phenobarbital St. John’s wort (Hypericum perforatum) | ↓Dolutegravir | Avoid coadministration with TRIUMEQ or TRIUMEQ PD because there are insufficient data to make dosing recommendations.
Medications containing polyvalent cations (e.g., Mg or Al):; Cation-containing antacidsa or laxatives; Sucralfate; Buffered medications | ↓Dolutegravir | Administer TRIUMEQ or TRIUMEQ PD 2 hours before or 6 hours after taking medications containing polyvalent cations.
Oral calcium and iron supplements, including multivitamins containing calcium or irona | ↓Dolutegravir | When taken with food, TRIUMEQ or TRIUMEQ PD and supplements or multivitamins containing calcium or iron can be taken at the same time. Under fasting conditions, TRIUMEQ or TRIUMEQ PD should be taken 2 hours before or 6 hours after taking supplements containing calcium or iron.
Metformina | ↑Metformin | Refer to the prescribing information for metformin for assessing the benefit and risk of concomitant use of TRIUMEQ or TRIUMEQ PD and metformin.
Rifampina | ↓Dolutegravir | In adults and in pediatric patients weighing at least 25 kg, adjust dolutegravir dose to 50 mg twice daily. An additional 50-mg dose of TIVICAY should be taken, separated by 12 hours from TRIUMEQ.; In pediatric patients weighing 6 to <25 kg, an additional weight-based dose of dolutegravir should be given separated by 12 hours from TRIUMEQ PD.; - 6 to <10 kg: administer an additional 15-mg dose of dolutegravir (3 TIVICAY PD tablets for oral suspension), 12 hours after TRIUMEQ PD. - 10 to <14 kg: administer an additional 20-mg dose of dolutegravir (4 TIVICAY PD tablets for oral suspension), 12 hours after TRIUMEQ PD. - 14 to <20 kg: administer an additional 25-mg dose of dolutegravir (5 TIVICAY PD tablets for oral suspension), 12 hours after TRIUMEQ PD. - 20 to <25 kg: administer an additional 30-mg dose of dolutegravir (6 TIVICAY PD tablets for oral suspension), 12 hours after TRIUMEQ PD.
a See Clinical Pharmacology (12.3) Table 8 or Table 10 for magnitude of interaction.

Methadone

Abacavir: In a trial of 11 HIV-1–infected subjects receiving methadone-maintenance therapy with 600 mg of abacavir twice daily (twice the currently recommended dose), oral methadone clearance increased [see Clinical Pharmacology (12.3)]. This alteration will not result in a methadone dose modification in the majority of patients; however, an increased methadone dose may be required in a small number of patients.

Sorbitol

Lamivudine: Coadministration of single doses of lamivudine and sorbitol resulted in a sorbitol dose-dependent reduction in lamivudine exposures. When possible, avoid use of sorbitol-containing medicines with lamivudine-containing medicines [see Clinical Pharmacology (12.3)].

Riociguat

Abacavir: Coadministration with TRIUMEQ resulted in increased riociguat exposure, which may increase the risk of riociguat adverse reactions [see Clinical Pharmacology (12.3)]. The riociguat dose may need to be reduced. See full prescribing information for ADEMPAS (riociguat).

8 USE IN SPECIFIC POPULATIONS

8.1 Pregnancy

Pregnancy Exposure Registry

There is a pregnancy exposure registry that monitors pregnancy outcomes in individuals exposed to TRIUMEQ during pregnancy. Healthcare providers are encouraged to register patients by calling the Antiretroviral Pregnancy Registry (APR) at 1‑800‑258‑4263.

Risk Summary

Data from two, ongoing birth outcome surveillance studies in Botswana and Eswatini which together include over 14,000 individuals evaluated during pregnancy show similar prevalence of neural tube defects among infants born to individuals taking dolutegravir at the time of conception compared to those born to individuals taking non-dolutegravir-containing regimens at conception or infants born to HIV-negative individuals (see Data).

There are insufficient human data on the use of TRIUMEQ during pregnancy to definitively assess a drug-associated risk for birth defects and miscarriage. However, available human data from the APR with the individual components of TRIUMEQ do not indicate an increased risk of birth defects (see Data). The background risk for major birth defects for the indicated population is unknown. In the U.S. general population, the estimated background rate for major birth defects and miscarriage in clinically recognized pregnancies is 2% to 4% and 15% to 20%, respectively.

In animal reproduction studies, no evidence of adverse developmental outcomes (including neural tube defects) was observed with dolutegravir at systemic exposures (AUC) less than (rabbits) and approximately 50 times (rats) the exposure in humans at the recommended human dose (RHD) (see Data). Oral administration of abacavir to pregnant rats during organogenesis resulted in fetal malformations and other embryonic and fetal toxicities at exposures 35 times the human exposure (AUC) at the RHD. No adverse developmental effects were observed following oral administration of abacavir to pregnant rabbits during organogenesis at exposures approximately 9 times the human exposure (AUC) at the RHD. Oral administration of lamivudine to pregnant rabbits during organogenesis resulted in embryolethality at a human exposure (AUC) similar to the RHD; however, no adverse development effects were observed with oral administration of lamivudine to pregnant rats during organogenesis at plasma concentrations (Cmax) 35 times the RHD (see Data).

Data

Human Data:

Dolutegravir:

Observational studies: The first interim analysis from an ongoing birth outcome surveillance study in Botswana identified an association between dolutegravir and an increased risk of neural tube defects when dolutegravir was administered at the time of conception and in early pregnancy. A subsequent analysis was conducted based on a larger cohort from the birth outcome surveillance study in Botswana and included over 9,460 individuals exposed to dolutegravir at conception, 23,664 individuals exposed to non-dolutegravir-containing regimens, and 170,723 HIV-negative pregnant individuals. The prevalence of neural tube defects in infants delivered to individuals taking dolutegravir at conception was 0.11% (95% CI: 0.05-0.19%). The observed prevalence rate did not differ significantly from that of infants delivered to individuals taking non-dolutegravir-containing regimens (0.11%, 95% CI: 0.07-0.16%), or to HIV-negative individuals (0.06%, 95% CI: 0.05-0.08%).

The Eswatini birth outcome surveillance study includes 9,743 individuals exposed to dolutegravir at conception, 1,838 individuals exposed to non-dolutegravir-containing regimens, and 32,259 HIV-negative pregnant individuals. The prevalence of neural tube defects in infants delivered to individuals taking dolutegravir at conception was 0.08% (95% CI: 0.04-0.16%). The observed prevalence rate did not differ significantly from that of infants delivered to individuals taking non-dolutegravir-containing regimens (0.22%, 95% CI: 0.06-0.56%) or to HIV-negative individuals (0.08%, 95% CI: 0.06-0.12%). The observed prevalence of neural tube defects in infants delivered to individuals taking non-dolutegravir-containing regimens had a wide confidence interval due to low sample size.

Limitations of these birth outcome surveillance studies include insufficient data to determine if baseline characteristics were balanced between the study groups or to assess other factors such as the use of folic acid during the preconception or first trimester periods.

Antiretroviral Pregnancy Registry: Based on prospective reports to the APR, of over 1,300 exposures to dolutegravir during pregnancy resulting in live births (including 874 exposed in the first trimester), the prevalence of defects in live births was 3.3% (95% CI: 2.2% to 4.7%) following first-trimester exposure to dolutegravir-containing regimens and 5.0% (95% CI: 3.2% to 7.3%) following second-/third-trimester exposure to dolutegravir-containing regimens. In the U.S. reference population of the Metropolitan Atlanta Congenital Defects Program (MACDP), the background birth defect rate was 2.7%.

Dolutegravir has been shown to cross the placenta. In a clinical trial in Uganda and South Africa in women during the last trimester of pregnancy receiving dolutegravir 50 mg once daily, the ratio of median dolutegravir concentration in fetal umbilical cord to that in maternal peripheral plasma was 1.21 (range 0.51-2.11) (n = 15).

Abacavir: Based on prospective reports to the APR of over 2,800 exposures to abacavir during pregnancy resulting in live births (including 1,455 exposed in the first trimester), there was no difference between the overall risk of birth defects for abacavir compared with the background birth defect rate of 2.7% in the U.S. reference population of the MACDP. The prevalence of defects in live births was 3.2% (95% CI: 2.4% to 4.3%) following first trimester exposure to abacavir-containing regimens and 3.0% (95% CI: 2.2% to 4.1%) following second/third trimester exposure to abacavir-containing regimens.

Abacavir has been shown to cross the placenta and concentrations in neonatal plasma at birth were essentially equal to those in maternal plasma at delivery [see Clinical Pharmacology (12.3)].

Lamivudine: Based on prospective reports to the APR of over 13,000 exposures to lamivudine during pregnancy resulting in live births (including 5,613 exposed in the first trimester), there was no difference between the overall risk of birth defects for lamivudine compared with the background birth defect rate of 2.7% in the U.S. reference population of the MACDP. The prevalence of birth defects in live births was 3.1% (95% CI: 2.6% to 3.6%) following first trimester exposure to lamivudine-containing regimens and 2.9% (95% CI: 2.5%, 3.3%) following second/third trimester exposure to lamivudine-containing regimens.

Lamivudine pharmacokinetics were studied in pregnant women during 2 clinical trials conducted in South Africa. The trials assessed pharmacokinetics in 16 women at 36 weeks’ gestation using 150 mg lamivudine twice daily with zidovudine, 10 women at 38 weeks’ gestation using 150 mg lamivudine twice daily with zidovudine, and 10 women at 38 weeks’ gestation using lamivudine 300 mg twice daily without other antiretrovirals. These trials were not designed or powered to provide efficacy information. Lamivudine concentrations were generally similar in maternal, neonatal, and umbilical cord serum samples. In a subset of subjects, amniotic fluid specimens were collected following natural rupture of membranes and confirmed that lamivudine crosses the placenta in humans. Based on limited data at delivery, median (range) amniotic fluid concentrations of lamivudine were 3.9-fold (1.2- to 12.8-fold) greater compared with paired maternal serum concentration (n = 8).

Animal Data:

Dolutegravir: Dolutegravir was administered orally to pregnant rats and rabbits (up to 1,000 mg/kg/day) on Gestation Days 6 to 17 and 6 to 18, respectively, and to rats on Gestation Day 6 to lactation/post-partum Day 20. No adverse effects on embryo-fetal (rats and rabbits) or pre/post-natal (rats) development were observed up to the highest dose tested. During organogenesis, systemic exposures (AUC) to dolutegravir in rabbits were less than the exposure in humans at the RHD and in rats were approximately 50 times the exposure in humans at the RHD. In the rat pre/post-natal development study, decreased body weight of the developing offspring was observed during lactation at a maternally toxic dose (approximately 50 times human exposure at the RHD).

Abacavir: Abacavir was administered orally to pregnant rats (at 100, 300, and 1,000 mg/kg/day) and rabbits (at 125, 350, or 700 mg/kg/day) during organogenesis (on Gestation Days 6 through 17 and 6 through 20, respectively). Fetal malformations (increased incidences of fetal anasarca and skeletal malformations) or developmental toxicity (decreased fetal body weight and crown‑rump length) were observed in rats at doses up to 1,000 mg/kg/day, resulting in exposures approximately 35 times the human exposure (AUC) at the RHD. No developmental effects were observed in rats at 100 mg/kg/day, resulting in exposures (AUC) 3.5 times the human exposure at the recommended daily dose. In a fertility and early embryo-fetal development study conducted in rats (at 60, 160, or 500 mg/kg/day), embryonic and fetal toxicities (increased resorptions, decreased fetal body weights) or toxicities to the offspring (increased incidence of stillbirth and lower body weights) occurred at doses up to 500 mg/kg/day. No developmental effects were observed in rats at 60 mg/kg/day, resulting in exposures (AUC) approximately 4 times the human exposure at the RHD. Studies in pregnant rats showed that abacavir is transferred to the fetus through the placenta. In pregnant rabbits, no developmental toxicities and no increases in fetal malformations occurred at up to the highest dose evaluated, resulting in exposures (AUC) approximately 9 times the human exposure at the RHD.

Lamivudine: Lamivudine was administered orally to pregnant rats (at 90, 600, and 4,000 mg/kg/day) and rabbits (at 90, 300 and 1,000 mg/kg/day and at 15, 40, and 90 mg/kg/day) during organogenesis (on Gestation Days 7 through 16 [rat] and 8 through 20 [rabbit]). No evidence of fetal malformations due to lamivudine was observed in rats and rabbits at doses producing plasma concentrations (Cmax) approximately 35 times higher than human exposure at the recommended daily dose. Evidence of early embryolethality was seen in the rabbit at systemic exposures (AUC) similar to those observed in humans, but there was no indication of this effect in the rat at plasma concentrations (Cmax) 35 times higher than human exposure at the recommended daily dose. Studies in pregnant rats showed that lamivudine is transferred to the fetus through the placenta. In the fertility/pre- and postnatal development study in rats, lamivudine was administered orally at doses of 180, 900, and 4,000 mg/kg/day (from prior to mating through postnatal Day 20). In the study, development of the offspring, including fertility and reproductive performance, were not affected by the maternal administration of lamivudine.

8.2 Lactation

Risk Summary

Abacavir, dolutegravir and lamivudine are present in human milk. There is no information on the effects of TRIUMEQ or its components on the breastfed infant or the effects of the drug on milk production.

Potential risks of breastfeeding include: (1) HIV‑1 transmission (in HIV-1–negative infants), (2) developing viral resistance (in HIV-1–positive infants), and (3) adverse reactions in a breastfed infant similar to those seen in adults.

8.4 Pediatric Use

The clinical data supporting use of TRIUMEQ and TRIUMEQ PD in pediatric patients with HIV-1 infection aged at least 3 months old weighing at least 6 kg is derived from the following previously conducted pediatric trials using TRIUMEQ and TRIUMEQ PD or the individual components:

- The safety, pharmacokinetics, and antiviral activity (efficacy) of TRIUMEQ and TRIUMEQ PD were established through an open-label, multicenter clinical trial (IMPAACT 2019), in which HIV-1–infected, treatment-naïve, or treatment-experienced, pediatric subjects younger than 12 years and weighing at least 6 kg to less than 40 kg were treated with TRIUMEQ or TRIUMEQ PD [see Adverse Reactions (6.1), Clinical Pharmacology (12.3), Clinical Studies (14.2)].
- The safety and efficacy of once-daily abacavir and lamivudine were established with a randomized, multicenter trial (ARROW [COL105677]) in HIV-1–infected, treatment-naive subjects aged 3 months to 17 years with a first-line regimen containing abacavir and lamivudine, using either the combination of EPIVIR and ZIAGEN or EPZICOM [see Adverse Reactions (6.1), Clinical Studies (14.2)].
- The safety, pharmacokinetics, and antiviral activity (efficacy) of TIVICAY and TIVICAY PD were established through an ongoing, open-label, multicenter, dose-finding clinical trial (IMPAACT P1093), in which HIV-1–infected, treatment-naive or treatment-experienced, INSTI-naive, pediatric and adolescent subjects aged 4 weeks to <18 years and weighing at least 3 kg were treated with TIVICAY or TIVICAY PD plus optimized background therapy [see Adverse Reactions (6.1), Clinical Pharmacology (12.3), Clinical Studies (14.2)].
- Additional pharmacokinetics data were evaluated in 2 pharmacokinetic substudies in ODYSSEY, an ongoing open-label, randomized, non-inferiority trial to evaluate the safety, efficacy, and pharmacokinetic parameters of TIVICAY or TIVICAY PD plus two nucleoside reverse transcriptase inhibitors (NRTIs) (mainly abacavir and lamivudine) compared with standard of care in HIV-1–infected pediatric subjects younger than 18 years [see Clinical Pharmacology (12.3)].

Overall, the safety, and efficacy profile of TRIUMEQ and TRIUMEQ PD in pediatric patients is comparable to that observed in adults. There are no data available on the use of lamivudine in pediatric patients with renal impairment [see Dosage and Administration (2.7), Warnings and Precautions (5.3), Adverse Reactions (6.1), Use in Specific Populations (8.6), Clinical Pharmacology (12.3), Clinical Studies (14.2)].

The safety and effectiveness of TRIUMEQ PD have not been established in pediatric patients aged less than 3 months or weighing less than 6 kg.

8.5 Geriatric Use

Clinical trials of abacavir, dolutegravir, or lamivudine did not include sufficient numbers of subjects aged 65 and over to determine whether they respond differently from younger subjects. In general, caution should be exercised in the administration of TRIUMEQ in elderly patients reflecting the greater frequency of decreased hepatic, renal, or cardiac function, and of concomitant disease or other drug therapy [see Clinical Pharmacology (12.3)].

8.6 Patients with Impaired Renal Function

TRIUMEQ and TRIUMEQ PD are not recommended for patients with creatinine clearance <30 mL/min and pediatric patients with a similar degree of renal impairment based on age-appropriate assessment of renal function because TRIUMEQ and TRIUMEQ PD are fixed-dose combinations, and the dosage of the individual components cannot be adjusted. If a dose reduction of lamivudine, a component of TRIUMEQ and TRIUMEQ PD, is required for patients with creatinine clearance <30 mL/min and in pediatric patients with a similar degree of renal impairment based on age-appropriate assessment of renal function, then the individual components should be used [see Clinical Pharmacology (12.3)].

Patients with a creatinine clearance between 30 and 49 mL/min receiving TRIUMEQ may experience a 1.6- to 3.3-fold higher lamivudine exposure (AUC) than patients with a creatinine clearance ≥50 mL/min. There are no safety data from randomized, controlled trials comparing TRIUMEQ to the individual components in patients with a creatinine clearance between 30 and 49 mL/min who received dose-adjusted lamivudine. Additionally, there are no data available on the use of lamivudine in pediatric patients with renal impairment. In the original lamivudine registrational trials in combination with zidovudine, higher lamivudine exposures were associated with higher rates of hematologic toxicities (neutropenia and anemia), although discontinuations due to neutropenia or anemia each occurred in <1% of subjects.

Patients with a sustained creatinine clearance between 30 and 49 mL/min or pediatric patients with a similar degree of renal impairment based on an age-appropriate assessment of renal function who receive TRIUMEQ or TRIUMEQ PD should be monitored for hematologic toxicities. If new or worsening neutropenia or anemia develop, dose adjustment of lamivudine, per lamivudine prescribing information, is recommended. If lamivudine dose adjustment is indicated, TRIUMEQ or TRIUMEQ PD should be discontinued, and the individual components should be used to construct the treatment regimen.

8.7 Patients with Impaired Hepatic Function

TRIUMEQ and TRIUMEQ PD are fixed-dose combinations, and the dosage of the individual components cannot be adjusted. If a dose reduction of abacavir, a component of TRIUMEQ and TRIUMEQ PD, is required for patients with mild hepatic impairment (Child-Pugh Score A), then the individual components should be used [see Clinical Pharmacology (12.3)].

The safety, efficacy, and pharmacokinetic properties of abacavir have not been established in patients with moderate (Child-Pugh Score B) or severe (Child-Pugh Score C) hepatic impairment; therefore, TRIUMEQ and TRIUMEQ PD are contraindicated in these patients [see Contraindications (4)].

10 OVERDOSAGE

There is no known specific treatment for overdose with TRIUMEQ or TRIUMEQ PD. If overdose occurs, the patient should be monitored, and standard supportive treatment applied as required.

Dolutegravir

As dolutegravir is highly bound to plasma proteins, it is unlikely that it will be significantly removed by dialysis.

Abacavir

It is not known whether abacavir can be removed by peritoneal dialysis or hemodialysis.

Lamivudine

Because a negligible amount of lamivudine was removed via (4-hour) hemodialysis, continuous ambulatory peritoneal dialysis, and automated peritoneal dialysis, it is not known if continuous hemodialysis would provide clinical benefit in a lamivudine overdose event.

11 DESCRIPTION

TRIUMEQ and TRIUMEQ PD

TRIUMEQ and TRIUMEQ PD contain an INSTI (dolutegravir) and 2 nucleoside analogues (abacavir and lamivudine) with inhibitory activity against HIV.

Each film-coated tablet of TRIUMEQ, for oral use, contains 600 mg of abacavir (present as 702 mg of abacavir sulfate), 50 mg of dolutegravir (present as 52.6 mg of dolutegravir sodium), and 300 mg of lamivudine. The inactive ingredients of TRIUMEQ tablets include D-mannitol, magnesium stearate, microcrystalline cellulose, povidone, and sodium starch glycolate. The tablet film‑coating contains the inactive ingredients iron oxide black, iron oxide red, macrogol/PEG, polyvinyl alcohol–part hydrolyzed, talc, and titanium oxide.

Each film-coated tablet of TRIUMEQ PD for oral suspension contains 60 mg of abacavir (present as 70.2 mg of abacavir sulfate), 5 mg of dolutegravir (present as 5.26 mg of dolutegravir sodium), and 30 mg of lamivudine. The inactive ingredients of TRIUMEQ PD tablets include acesulfame potassium, crospovidone, mannitol, microcrystalline cellulose, povidone K29/32, silicified microcrystalline cellulose, sodium starch glycolate, sodium stearyl fumarate, strawberry cream flavor and sucralose. The tablet film-coating contains the inactive ingredients: ferric oxide yellow, macrogol/PEG, polyvinyl alcohol-part hydrolyzed, talc and titanium dioxide.

Abacavir Sulfate

The chemical name of abacavir sulfate is (1S,cis)-4-[2-amino-6-(cyclopropylamino)-9H-purin-9-yl]-2-cyclopentene-1-methanol sulfate (salt) (2:1). It has a molecular formula of (C14H18N6O)2•H2SO4 and a molecular weight of 670.76 g/mol. It has the following structural formula:

Abacavir sulfate is a white to off-white solid and is soluble in water.

Dolutegravir Sodium

The chemical name of dolutegravir sodium is sodium (4R,12aS)-9-{[(2,4-difluorophenyl)methyl]carbamoyl}-4-methyl-6,8-dioxo-3,4,6,8,12,12a-hexahydro-2H-pyrido[1',2':4,5]pyrazino[2,1-b][1,3]oxazin-7-olate. The empirical formula is C20H18F2N3NaO5 and the molecular weight is 441.36 g/mol. It has the following structural formula:

Dolutegravir sodium is a white to light yellow powder and is slightly soluble in water.

Lamivudine

The chemical name of lamivudine is (2R,cis)-4-amino-1-(2-hydroxymethyl-1,3-oxathiolan-5-yl)-(1H)-pyrimidin-2-one. Lamivudine is the (‑)enantiomer of a dideoxy analogue of cytidine. Lamivudine has also been referred to as (‑)2′,3′-dideoxy, 3′-thiacytidine. It has a molecular formula of C8H11N3O3S and a molecular weight of 229.3 g/mol. It has the following structural formula:

Lamivudine is a white to off-white crystalline solid and is soluble in water.

12 CLINICAL PHARMACOLOGY

12.1 Mechanism of Action

TRIUMEQ and TRIUMEQ PD are a fixed-dose combination of the HIV‑1 antiretroviral agents abacavir, dolutegravir, and lamivudine [see Microbiology (12.4)].

12.2 Pharmacodynamics

Effects on Electrocardiogram

A thorough QT trial has been conducted for dolutegravir. Neither the effects of abacavir nor lamivudine as single entities or the combination of abacavir, dolutegravir, and lamivudine on the QT interval have been evaluated.

In a randomized, placebo-controlled, cross-over trial, 42 healthy subjects received single-dose oral administrations of placebo, dolutegravir 250‑mg suspension (exposures approximately 3–fold of the 50-mg once-daily dose at steady state), and moxifloxacin 400 mg (active control) in random sequence. After baseline and placebo adjustment, the maximum mean QTc change based on Fridericia correction method (QTcF) for dolutegravir was 2.4 msec (1-sided 95% upper CI: 4.9 msec). Dolutegravir did not prolong the QTc interval over 24 hours postdose.

Effects on Renal Function

The effect of dolutegravir on renal function was evaluated in an open-label, randomized, 3-arm, parallel, placebo-controlled trial in healthy subjects (n = 37) who received dolutegravir 50 mg once daily (n = 12), dolutegravir 50 mg twice daily (n = 13), or placebo once daily (n = 12) for 14 days. A decrease in creatinine clearance, as determined by 24-hour urine collection, was observed with both doses of dolutegravir after 14 days of treatment in subjects who received 50 mg once daily (9% decrease) and 50 mg twice daily (13% decrease). Neither dose of dolutegravir had a significant effect on the actual glomerular filtration rate (determined by the clearance of probe drug, iohexol) or effective renal plasma flow (determined by the clearance of probe drug, para-amino hippurate) compared with the placebo.

12.3 Pharmacokinetics

Pharmacokinetics in Adults

One TRIUMEQ tablet was bioequivalent to one dolutegravir (TIVICAY) tablet (50 mg) plus one abacavir and lamivudine fixed-dose combination tablet (EPZICOM) under fasted conditions in healthy subjects (n = 62).

TRIUMEQ tablets and TRIUMEQ PD tablets for oral suspension are bioequivalent for the abacavir and lamivudine components, but not for the dolutegravir component. The relative dolutegravir bioavailability of TRIUMEQ PD is approximately 1.7-fold higher than TRIUMEQ; therefore, the 2 dosage forms are not substitutable on a milligram-per-milligram basis [see Dosage and Administration (2.3), Warnings and Precautions (5.7)]. The relative dolutegravir bioavailability is expected to be similar between TRIUMEQ PD and TIVICAY PD.

Abacavir: Following oral administration, abacavir is rapidly absorbed and extensively distributed. After oral administration of a single dose of 600 mg of abacavir in 20 subjects, Cmax was 4.26 ± 1.19 mcg/mL (mean ± SD) and AUC∞ was 11.95 ± 2.51 mcg•hour/mL. Binding of abacavir to human plasma proteins is approximately 50% and was independent of concentration. Total blood and plasma drug‑related radioactivity concentrations are identical, demonstrating that abacavir readily distributes into erythrocytes. The primary routes of elimination of abacavir are metabolism by alcohol dehydrogenase to form the 5′‑carboxylic acid and glucuronyl transferase to form the 5′‑glucuronide. In single-dose trials, the observed elimination half-life (t½) was 1.54 ± 0.63 hours. After intravenous administration, total clearance was 0.80 ± 0.24 L/h/kg (mean ± SD).

Dolutegravir: Following oral administration of dolutegravir, peak plasma concentrations were observed 2 to 3 hours postdose. With once-daily dosing, pharmacokinetic steady state is achieved within approximately 5 days with average accumulation ratios for AUC, Cmax, and C24 h ranging from 1.2 to 1.5. Dolutegravir is a P-gp substrate in vitro. The absolute bioavailability of dolutegravir has not been established. Dolutegravir is highly bound (≥98.9%) to human plasma proteins based on in vivo data and binding is independent of plasma concentration of dolutegravir. The apparent volume of distribution (Vd/F) following 50-mg once-daily administration is estimated at 17.4 L based on a population pharmacokinetic analysis.

Dolutegravir is primarily metabolized via UGT1A1 with some contribution from CYP3A. After a single oral dose of [^14C] dolutegravir, 53% of the total oral dose is excreted unchanged in the feces. Thirty-one percent of the total oral dose is excreted in the urine, represented by an ether glucuronide of dolutegravir (18.9% of total dose), a metabolite formed by oxidation at the benzylic carbon (3.0% of total dose), and its hydrolytic N-dealkylation product (3.6% of total dose). Renal elimination of unchanged drug was <1% of the dose. Dolutegravir has a terminal half-life of approximately 14 hours and an apparent clearance (CL/F) of 1.0 L/h based on population pharmacokinetic analyses.

The pharmacokinetic properties of dolutegravir have been evaluated in healthy adult subjects and HIV‑1–infected adult subjects. Exposure to dolutegravir was generally similar between healthy subjects and HIV‑1–infected subjects.

Table 7. Dolutegravir Steady-State Pharmacokinetic Parameter Estimates in HIV-1–Infected Adults
Parameter | 50 mg Once Daily Geometric Mean (%CV)
AUC(0-24) (mcg•h/mL) | 53.6 (27)
Cmax (mcg/mL) | 3.67 (20)
Cmin (mcg/mL) | 1.11 (46)

Cerebrospinal Fluid (CSF): In 11 treatment-naive subjects on dolutegravir 50 mg daily plus abacavir/lamivudine, the median dolutegravir concentration in CSF was 18 ng/mL (range: 4 ng/mL to 23.2 ng/mL) 2 to 6 hours postdose after 2 weeks of treatment. The clinical relevance of this finding has not been established.

Lamivudine: Following oral administration, lamivudine is rapidly absorbed and extensively distributed. After multiple‑dose oral administration of lamivudine 300 mg once daily for 7 days to 60 healthy subjects, steady-state Cmax (Cmax,ss) was 2.04 ± 0.54 mcg/mL (mean ± SD) and the 24‑hour steady‑state AUC (AUC24,ss) was 8.87 ± 1.83 mcg•hour/mL. Binding to plasma protein is low. Approximately 70% of an intravenous dose of lamivudine is recovered as unchanged drug in the urine. Metabolism of lamivudine is a minor route of elimination. In humans, the only known metabolite is the trans‑sulfoxide metabolite (approximately 5% of an oral dose after 12 hours). In most single-dose trials with plasma sampling up to 48 or 72 hours after dosing, the observed mean elimination half-life (t½) ranged from 13 to 19 hours. In HIV-1–infected subjects, total clearance was 398.5 ± 69.1 mL/min (mean ± SD).

Effect of Food on Oral Absorption

TRIUMEQ or TRIUMEQ PD may be taken with or without food. Overall, when compared with fasted conditions, administration of TRIUMEQ to healthy adult subjects with a high-fat meal (53% fat, 869 calories) resulted in decreased Cmax for abacavir and increased Cmax and AUC for dolutegravir. Lamivudine exposures were not affected by food. With a high-fat meal, the Cmax of abacavir decreased 23% and the Cmax and AUC of dolutegravir increased 37% and 48%, respectively. When compared with fasted conditions, administration of TRIUMEQ PD to healthy adult subjects with a high-fat meal (50% fat, 917 calories) resulted in decreased Cmax for abacavir (55%), dolutegravir (29%) and lamivudine (36%). AUCs for all 3 components were not affected by food.

Specific Populations

Patients with Renal Impairment: The pharmacokinetics for the individual components of TRIUMEQ and TRIUMEQ PD have been evaluated in patients with renal impairment (see the U.S. prescribing information for the individual abacavir, dolutegravir, and lamivudine components).

Patients with Hepatic Impairment: The pharmacokinetics for the individual components of TRIUMEQ and TRIUMEQ PD have been evaluated in patients with varying degrees of hepatic impairment (see the U.S. prescribing information for the individual abacavir, dolutegravir, and lamivudine components).

Pregnant women: Abacavir: Abacavir pharmacokinetics were studied in 25 pregnant women during the last trimester of pregnancy receiving abacavir 300 mg twice daily. Abacavir exposure (AUC) during pregnancy was similar to those in postpartum and in HIV-infected non-pregnant historical controls. Consistent with passive diffusion of abacavir across the placenta, abacavir concentrations in neonatal plasma cord samples at birth were essentially equal to those in maternal plasma at delivery.

Lamivudine: Lamivudine pharmacokinetics were studied in 36 pregnant women during 2 clinical trials conducted in South Africa. Lamivudine pharmacokinetics in pregnant women were similar to those seen in non-pregnant adults and in postpartum women. Lamivudine concentrations were generally similar in maternal, neonatal, and umbilical cord serum samples.

Pediatric Patients: The pharmacokinetics of TRIUMEQ, TRIUMEQ PD (abacavir, dolutegravir, and lamivudine) and their individual components have been evaluated in pediatric subjects.

Abacavir, Dolutegravir and Lamivudine: The pharmacokinetics of TRIUMEQ and TRIUMEQ PD were evaluated in the IMPAACT 2019 trial. Steady-state plasma exposure at doses by weight band are summarized in Table 8 [see Use in Specific Populations (8.4), Clinical Studies (14.2)].

Overall, exposures of abacavir, dolutegravir and lamivudine at the recommended doses for TRIUMEQ PD and TRIUMEQ are within the observed exposure ranges at the recommended doses of individual products in adults and pediatrics. Refer to the prescribing information for EPIVIR, TIVICAY, and ZIAGEN for pharmacokinetic information on lamivudine, dolutegravir, and abacavir, respectively, in pediatric patients.

Table 8. Summary of Pharmacokinetic Parameters in Pediatric HIV-1–Infected Subjects (IMPAACT 2019 Trial)
Drug | Weight Band | Dosea of single entities in TRIUMEQ or TRIUMEQ PD | n | Pharmacokinetic Parameter; Geometric Mean (%CV)
Drug | Weight Band | Dosea of single entities in TRIUMEQ or TRIUMEQ PD | n | Cmax; (mcg/mL) | AUC0-24h; (mcg∙h/mL) | C24h; (ng/mL)
Abacavir | 6 to <10 kg | 180 mg once daily TRIUMEQ PD | 7 | 7.30 (20) | 17.7 (34) | 3 (128)
Abacavir | 10 to <14 kg | 240 mg once daily; TRIUMEQ PD | 7 | 8.36 (44) | 19.8 (51) | 5 (127)
Abacavir | 14 to <20 kg | 300 mg once daily; TRIUMEQ PD | 7 | 6.26 (31) | 15.1 (40) | 3 (108)
Abacavir | 20 to <25 kg | 360 mg once daily; TRIUMEQ PD | 7 | 6.65 (28) | 17.4 (19) | 4 (85)
Abacavir | 25 to <40 kg | 600 mg once daily; TRIUMEQ | 7 | 9.04 (22) | 25.7 (15) | 11 (229)
Dolutegravir | 6 to <10 kg | 15 mg once daily TRIUMEQ PD | 7 | 7.40 (28) | 75.9 (34) | 910 (68)
Dolutegravir | 10 to <14 kg | 20 mg once daily; TRIUMEQ PD | 7 | 8.85 (21) | 91.0 (36) | 1220 (77)
Dolutegravir | 14 to <20 kg | 25 mg once daily; TRIUMEQ PD | 7 | 7.04 (17) | 71.4 (23) | 790 (44)
Dolutegravir | 20 to <25 kg | 30 mg once daily; TRIUMEQ PD | 7 | 7.29 (17) | 84.4 (26) | 1350 (95)
Dolutegravir | 25 to <40 kg | 50 mg once daily; TRIUMEQ | 7 | 6.25 (21) | 71.8 (14) | 980 (28)
Lamivudine | 6 to <10 kg | 90 mg once daily TRIUMEQ PD | 7 | 2.29 (40) | 10.7 (46) | 55 (39)
Lamivudine | 10 to <14 kg | 120 mg once daily; TRIUMEQ PD | 7 | 3.55 (19) | 14.2 (24) | 46 (48)
Lamivudine | 14 to <20 kg | 150 mg once daily; TRIUMEQ PD | 7 | 2.92 (23) | 13.0 (16) | 58 (37)
Lamivudine | 20 to <25 kg | 180 mg once daily; TRIUMEQ PD | 7 | 2.99 (32) | 14.5 (17) | 60 (18)
Lamivudine | 25 to <40 kg | 300 mg once daily; TRIUMEQ | 7 | 4.15 (29) | 21.7 (26) | 84 (35)
%CV, coefficient of variation expressed as a percentage.
a The relative dolutegravir bioavailability of TRIUMEQ PD tablets for oral suspension is ~1.7-fold that of TRIUMEQ tablets.

Geriatric Patients: Population analyses using pooled pharmacokinetic data from adult trials indicated age had no clinically relevant effect on the pharmacokinetics of dolutegravir. The pharmacokinetics of abacavir or lamivudine have not been studied in subjects older than 65 years.

Male and Female Patients: There are no significant or clinically relevant gender differences in the pharmacokinetics of the individual components (dolutegravir, abacavir, or lamivudine) based on the available information that was analyzed for each of the individual components.

Racial Groups: There are no significant or clinically relevant racial differences in pharmacokinetics of the individual components (dolutegravir, abacavir, or lamivudine) based on the available information that was analyzed for each of the individual components.

Drug Interaction Studies

The drug interaction trials described were conducted with dolutegravir, abacavir, and/or lamivudine as single entities; no drug interaction trials have been conducted using the combination of abacavir, dolutegravir, and lamivudine. No clinically significant drug interactions are expected between dolutegravir, abacavir, and lamivudine.

Dosing recommendations as a result of established and other potentially significant drug-drug interactions with the individual components of TRIUMEQ and TRIUMEQ PD are provided in Section 7.3 [see Drug Interactions (7)].

Table 9. Summary of Effect of Dolutegravir on the Pharmacokinetics of Coadministered Drugs
Coadministered Drug(s) and Dose(s) | Dose of Dolutegravir | n | Geometric Mean Ratio (90% CI) of Pharmacokinetic Parameters of Coadministered Drug with/without Dolutegravir No Effect = 1.00
Coadministered Drug(s) and Dose(s) | Dose of Dolutegravir | n | Cmax | AUC | Cτ or C24
Ethinyl estradiol 0.035 mg | 50 mg twice daily | 15 | 0.99 (0.91 to 1.08) | 1.03 (0.96 to 1.11) | 1.02 (0.93 to 1.11)
Metformin 500 mg twice daily | 50 mg once daily | 15a | 1.66 (1.53 to 1.81) | 1.79 (1.65 to 1.93) | _
Metformin 500 mg twice daily | 50 mg twice daily | 15a | 2.11 (1.91 to 2.33) | 2.45 (2.25 to 2.66) | _
Methadone 16 to 150 mg | 50 mg twice daily | 11 | 1.00 (0.94 to 1.06) | 0.98 (0.91 to 1.06) | 0.99 (0.91 to 1.07)
Midazolam 3 mg | 25 mg once daily | 10 | _ | 0.95 (0.79 to 1.15) | _
Norelgestromin 0.25 mg | 50 mg twice daily | 15 | 0.89 (0.82 to 0.97) | 0.98 (0.91 to 1.04) | 0.93 (0.85 to 1.03)
Rilpivirine 25 mg once daily | 50 mg once daily | 16 | 1.10 (0.99 to 1.22) | 1.06 (0.98 to 1.16) | 1.21 (1.07 to 1.38)
Tenofovir disoproxil fumarate 300 mg once daily | 50 mg once daily | 15 | 1.09 (0.97 to 1.23) | 1.12 (1.01 to 1.24) | 1.19 (1.04 to 1.35)
a The number of subjects represents the maximum number of subjects that were evaluated.

Table 10. Summary of Effect of Coadministered Drugs on the Pharmacokinetics of Dolutegravir
Coadministered Drug(s); and Dose(s) | Dose of Dolutegravir | n | Geometric Mean Ratio (90% CI) of Dolutegravir Pharmacokinetic Parameters with/without Coadministered Drugs No Effect = 1.00
Coadministered Drug(s); and Dose(s) | Dose of Dolutegravir | n | Cmax | AUC | Cτ or C24
Atazanavir; 400 mg once daily | 30 mg once daily | 12 | 1.50 (1.40 to 1.59) | 1.91 (1.80 to 2.03) | 2.80 (2.52 to 3.11)
Atazanavir/ritonavir; 300/100 mg once daily | 30 mg once daily | 12 | 1.34 (1.25 to 1.42) | 1.62 (1.50 to 1.74) | 2.21 (1.97 to 2.47)
Darunavir/ritonavir; 600/100 mg twice daily | 30 mg once daily | 15 | 0.89 (0.83 to 0.97) | 0.78 (0.72 to 0.85) | 0.62 (0.56 to 0.69)
Efavirenz; 600 mg once daily | 50 mg once daily | 12 | 0.61 (0.51 to 0.73) | 0.43 (0.35 to 0.54) | 0.25 (0.18 to 0.34)
Etravirine; 200 mg twice daily | 50 mg once daily | 16 | 0.48 (0.43 to 0.54) | 0.29 (0.26 to 0.34) | 0.12 (0.09 to 0.16)
Etravirine + darunavir/ritonavir; 200 mg + 600/100 mg twice daily | 50 mg once daily | 9 | 0.88 (0.78 to 1.00) | 0.75 (0.69 to 0.81) | 0.63 (0.52 to 0.76)
Etravirine + lopinavir/ritonavir; 200 mg + 400/100 mg twice daily | 50 mg once daily | 8 | 1.07 (1.02 to 1.13) | 1.11 (1.02 to 1.20) | 1.28 (1.13 to 1.45)
Fosamprenavir/ritonavir; 700 mg/100 mg twice daily | 50 mg once daily | 12 | 0.76 (0.63 to 0.92) | 0.65 (0.54 to 0.78) | 0.51 (0.41 to 0.63)
Lopinavir/ritonavir; 400/100 mg twice daily | 30 mg once daily | 15 | 1.00 (0.94 to 1.07) | 0.97 (0.91 to 1.04) | 0.94 (0.85 to 1.05)
Rilpivirine; 25 mg once daily | 50 mg once daily | 16 | 1.13 (1.06 to 1.21) | 1.12 (1.05 to 1.19) | 1.22 (1.15 to 1.30)
Tenofovir; 300 mg once daily | 50 mg once daily | 15 | 0.97 (0.87 to 1.08) | 1.01 (0.91 to 1.11) | 0.92; (0.82 to 1.04)
Tipranavir/ritonavir; 500/200 mg twice daily | 50 mg once daily | 14 | 0.54 (0.50 to 0.57) | 0.41 (0.38 to 0.44) | 0.24 (0.21 to 0.27)
Antacid (MAALOX); simultaneous administration | 50 mg single dose | 16 | 0.28 (0.23 to 0.33) | 0.26 (0.22 to 0.32) | 0.26 (0.21 to 0.31)
Antacid (MAALOX); 2 h after dolutegravir | 50 mg single dose | 16 | 0.82 (0.69 to 0.98) | 0.74 (0.62 to 0.90) | 0.70 (0.58 to 0.85)
Boceprevir; 800 mg every 8 h | 50 mg once daily | 13 | 1.05 (0.96 to 1.15) | 1.07 (0.95 to 1.20) | 1.08 (0.91 to 1.28)
Calcium carbonate 1,200 mg; simultaneous administration (fasted) | 50 mg single dose | 12 | 0.63 (0.50 to 0.81) | 0.61 (0.47 to 0.80) | 0.61 (0.47 to 0.80)
Calcium carbonate 1,200 mg; simultaneous administration (fed) | 50 mg single dose | 11 | 1.07 (0.83 to 1.38) | 1.09 (0.84 to 1.43) | 1.08 (0.81 to 1.42)
Calcium carbonate 1,200 mg; 2 h after dolutegravir | 50 mg single dose | 11 | 1.00 (0.78 to 1.29) | 0.94 (0.72 to 1.23) | 0.90 (0.68 to 1.19)
Carbamazepine; 300 mg twice daily | 50 mg once daily | 16c | 0.67 (0.61 to 0.73) | 0.51 (0.48 to 0.55) | 0.27 (0.24 to 0.31)
Ferrous fumarate 324 mg; simultaneous administration (fasted) | 50 mg single dose | 11 | 0.43 (0.35 to 0.52) | 0.46 (0.38 to 0.56) | 0.44 (0.36 to 0.54)
Ferrous fumarate 324 mg; simultaneous administration (fed) | 50 mg single dose | 11 | 1.03 (0.84 to 1.26) | 0.98 (0.81 to 1.20) | 1.00 (0.81 to 1.23)
Ferrous fumarate 324 mg; 2 h after dolutegravir | 50 mg single dose | 10 | 0.99 (0.81 to 1.21) | 0.95 (0.77 to 1.15) | 0.92 (0.74 to 1.13)
Multivitamin (One-A-Day); simultaneous administration | 50 mg single dose | 16 | 0.65 (0.54 to 0.77) | 0.67 (0.55 to 0.81) | 0.68 (0.56 to 0.82)
Omeprazole; 40 mg once daily | 50 mg single dose | 12 | 0.92 (0.75 to 1.11) | 0.97 (0.78 to 1.20) | 0.95 (0.75 to 1.21)
Prednisone; 60 mg once daily with taper | 50 mg once daily | 12 | 1.06 (0.99 to 1.14) | 1.11 (1.03 to 1.20) | 1.17 (1.06 to 1.28)
Rifampina; 600 mg once daily | 50 mg twice daily | 11 | 0.57 (0.49 to 0.65) | 0.46 (0.38 to 0.55) | 0.28 (0.23 to 0.34)
Rifampinb; 600 mg once daily | 50 mg twice daily | 11 | 1.18 (1.03 to 1.37) | 1.33 (1.15 to 1.53) | 1.22 (1.01 to 1.48)
Rifabutin; 300 mg once daily | 50 mg once daily | 9 | 1.16 (0.98 to 1.37) | 0.95 (0.82 to 1.10) | 0.70 (0.57 to 0.87)
a Comparison is rifampin taken with dolutegravir 50 mg twice daily compared with dolutegravir 50 mg twice daily.
b Comparison is rifampin taken with dolutegravir 50 mg twice daily compared with dolutegravir 50 mg once daily.
c The number of subjects represents the maximum number of subjects that were evaluated.

Abacavir or Lamivudine: The drug interactions described are based on trials conducted with abacavir or lamivudine as single entities.

Effect of Abacavir and Lamivudine on the Pharmacokinetics of Other Agents: In vitro studies have shown that abacavir has potential to inhibit CYP1A1 and limited potential to inhibit metabolism mediated by CYP3A4. Lamivudine does not inhibit or induce CYP3A4. Abacavir and lamivudine do not inhibit or induce other CYP enzymes (such as CYP2C9 or CYP2D6). Based on in vitro study results, abacavir and lamivudine at therapeutic drug exposures are not expected to affect the pharmacokinetics of drugs that are substrates of the following transporters: OATP1B1/3, BCRP or P-gp, OCT1, OCT2, OCT3 (lamivudine only), or MATE1 and MATE2‑K.

Abacavir, Dolutegravir, and Lamivudine: Coadministration of a single dose of riociguat (0.5 mg) to HIV-1–infected subjects receiving TRIUMEQ is reported to increase riociguat AUC(∞) compared with riociguat AUC(∞) reported in healthy subjects due to CYP1A1 inhibition by abacavir. The exact magnitude of increase in riociguat exposure has not been fully characterized based on findings from two studies [see Drug Interactions (7.3)].

Effect of Other Agents on the Pharmacokinetics of Abacavir or Lamivudine: In vitro, abacavir is not a substrate of OATP1B1, OATP1B3, OCT1, OCT2, OAT1, MATE1, MATE2-K, MRP2 or MRP4; therefore, drugs that modulate these transporters are not expected to affect abacavir plasma concentrations. Abacavir is a substrate of BCRP and P-gp in vitro; however, considering its absolute bioavailability (83%), modulators of these transporters are unlikely to result in a clinically relevant impact on abacavir concentrations.

Lamivudine is a substrate of MATE1, MATE2-K, and OCT2 in vitro. Trimethoprim (an inhibitor of these drug transporters) has been shown to increase lamivudine plasma concentrations. This interaction is not considered clinically significant as no dose adjustment of lamivudine is needed.

Lamivudine is a substrate of P-gp and BCRP; however, considering its absolute bioavailability (87%), it is unlikely that these transporters play a significant role in the absorption of lamivudine. Therefore, coadministration of drugs that are inhibitors of these efflux transporters is unlikely to affect the disposition and elimination of lamivudine.

Ethanol: Abacavir has no effect on the pharmacokinetic properties of ethanol. Ethanol decreases the elimination of abacavir causing an increase in overall exposure.

Interferon Alfa: There was no significant pharmacokinetic interaction between lamivudine and interferon alfa in a trial of 19 healthy male subjects.

Methadone: In a trial of 11 HIV‑1–infected subjects receiving methadone‑maintenance therapy (40 mg and 90 mg daily), with 600 mg of abacavir twice daily (twice the currently recommended dose), oral methadone clearance increased 22% (90% CI: 6% to 42%) [see Drug Interactions (7.3)]. The addition of methadone has no clinically significant effect on the pharmacokinetic properties of abacavir.

Ribavirin: In vitro data indicate ribavirin reduces phosphorylation of lamivudine, stavudine, and zidovudine. However, no pharmacokinetic (e.g., plasma concentrations or intracellular triphosphorylated active metabolite concentrations) or pharmacodynamic (e.g., loss of HIV‑1/HCV [hepatitis C virus] virologic suppression) interaction was observed when ribavirin and lamivudine (n = 18), stavudine (n = 10), or zidovudine (n = 6) were coadministered as part of a multi‑drug regimen to HIV‑1/HCV co‑infected subjects.

Sorbitol (Excipient): Lamivudine and sorbitol solutions were coadministered to 16 healthy adult subjects in an open-label, randomized-sequence, 4-period, crossover trial. Each subject received a single 300-mg dose of lamivudine oral solution alone or coadministered with a single dose of 3.2 g, 10.2 g, or 13.4 g of sorbitol in solution. Coadministration of lamivudine with sorbitol resulted in dose-dependent decreases of 20%, 39%, and 44% in the AUC(0-24); 14%, 32%, and 36% in the AUC(∞); and 28%, 52%, and 55% in the Cmax; of lamivudine, respectively.

Abacavir, Lamivudine, Zidovudine: Fifteen HIV‑1–infected subjects were enrolled in a crossover-designed drug interaction trial evaluating single doses of abacavir (600 mg), lamivudine (150 mg), and zidovudine (300 mg) alone or in combination. Analysis showed no clinically relevant changes in the pharmacokinetics of abacavir with the addition of lamivudine or zidovudine or the combination of lamivudine and zidovudine. Lamivudine exposure (AUC decreased 15%) and zidovudine exposure (AUC increased 10%) did not show clinically relevant changes with concurrent abacavir.

Lamivudine and Zidovudine: No clinically significant alterations in lamivudine or zidovudine pharmacokinetics were observed in 12 asymptomatic HIV‑1–infected adult patients given a single dose of zidovudine (200 mg) in combination with multiple doses of lamivudine (300 mg every 12 hours).

The effects of other coadministered drugs on abacavir or lamivudine are provided in Table 11.

Table 11. Effect of Coadministered Drugs on Abacavir or Lamivudine
Coadministered Drug and Dose | Drug and Dose | n | Concentrations of Abacavir or Lamivudine |  | Concentration of Coadministered Drug
Coadministered Drug and Dose | Drug and Dose | n | AUC | Variability | Concentration of Coadministered Drug
Ethanol; 0.7 g/kg | Abacavir; Single 600 mg | 24 | ↑41% | 90% CI:; 35% to 48% | ↔a
Nelfinavir; 750 mg every 8 h x 7 to 10 days | Lamivudine; Single 150 mg | 11 | ↑10% | 95% CI:; 1% to 20% | ↔
Trimethoprim 160 mg/; Sulfamethoxazole; 800 mg daily x 5 days | Lamivudine; Single 300 mg | 14 | ↑43% | 90% CI:; 32% to 55% | ↔
↑ = Increase; ↔ = No significant change.
a The drug-drug interaction was only evaluated in males.

12.4 Microbiology

Mechanism of Action

Dolutegravir: Dolutegravir inhibits HIV integrase by binding to the integrase active site and blocking the strand transfer step of retroviral DNA integration which is essential for the HIV replication cycle. Strand transfer biochemical assays using purified recombinant HIV‑1 integrase and pre-processed substrate DNA resulted in IC50 values of 2.7 nM and 12.6 nM.

Abacavir: Abacavir is a carbocyclic synthetic nucleoside analogue. Abacavir is converted by cellular enzymes to the active metabolite, carbovir triphosphate (CBV‑TP), an analogue of deoxyguanosine‑5′‑triphosphate (dGTP). CBV‑TP inhibits the activity of HIV‑1 reverse transcriptase (RT) both by competing with the natural substrate dGTP and by its incorporation into viral DNA.

Lamivudine: Lamivudine is a synthetic nucleoside analogue. Intracellularly lamivudine is phosphorylated to its active 5′-triphosphate metabolite, lamivudine triphosphate (3TC‑TP). The principal mode of action of 3TC‑TP is inhibition of RT via DNA chain termination after incorporation of the nucleotide analogue.

Antiviral Activity in Cell Culture

Dolutegravir: Dolutegravir exhibited antiviral activity against laboratory strains of wild-type HIV‑1 with mean concentration of drug necessary to affect viral replication by 50% (EC50) values of 0.5 nM (0.21 ng/mL) to 2.1 nM (0.85 ng/mL) in peripheral blood mononuclear cells (PBMCs) and MT-4 cells. Dolutegravir exhibited antiviral activity against 13 clinically diverse clade B isolates with a median EC50 value of 0.54 nM (range: 0.41 to 0.60 nM) in a viral susceptibility assay using the integrase coding region from clinical isolates. Dolutegravir demonstrated antiviral activity in cell culture against a panel of HIV‑1 clinical isolates with median EC50 values of 0.18 nM (n = 3, range: 0.09 to 0.5 nM), 0.08 nM (n = 5, range: 0.05 to 2.14 nM), 0.12 nM (n = 4, range: 0.05 to 0.51 nM), 0.17 nM (n = 3, range: 0.16 to 0.35 nM), 0.24 nM (n = 3, range: 0.09 to 0.32 nM), 0.17 nM (n = 4, range: 0.07 to 0.44 nM), 0.2 nM (n = 3, range: 0.02 to 0.87 nM), and 0.42 nM (n = 3, range: 0.41 to 1.79 nM) for clades A, B, C, D, E, F, and G, and group O viruses, respectively. Dolutegravir EC50 values against three HIV-2 clinical isolates in PBMC assays ranged from 0.09 nM to 0.61 nM.

Abacavir: The antiviral activity of abacavir against HIV‑1 was assessed in a number of cell lines including in primary monocytes/macrophages and PBMCs. EC50 values ranged from 3,700 to 5,800 nM (1 nM = 0.28 ng/mL) and 70 to 1,000 nM against HIV‑1IIIB and HIV‑1BaL, respectively, and the mean EC50 value was 260 ± 180 nM against 8 clinical isolates. The median EC50 values of abacavir were 344 nM (range: 14.8 to 676 nM), 16.9 nM (range: 5.9 to 27.9 nM), 8.1 nM (range: 1.5 to 16.7 nM), 356 nM (range: 35.7 to 396 nM), 105 nM (range: 28.1 to 168 nM), 47.6 nM (range: 5.2 to 200 nM), 51.4 nM (range: 7.1 to 177 nM), and 282 nM (range: 22.4 to 598 nM) against HIV‑1 clades A to G and group O viruses (n = 3 except n = 2 for clade B), respectively. The EC50 values against HIV‑2 isolates (n = 4), ranged from 24 to 490 nM.

Lamivudine: The antiviral activity of lamivudine against HIV‑1 was assessed in a number of cell lines including monocytes and PBMCs using standard susceptibility assays. EC50 values were in the range of 3 to 15,000 nM (1 nM = 0.23 ng/mL). The median EC50 values of lamivudine were 60 nM (range: 20 to 70 nM), 35 nM (range: 30 to 40 nM), 30 nM (range: 20 to 90 nM), 20 nM (range: 3 to 40 nM), 30 nM (range: 1 to 60 nM), 30 nM (range: 20 to 70 nM), 30 nM (range: 3 to 70 nM), and 30 nM (range: 20 to 90 nM) against HIV‑1 clades A to G and group O viruses (n = 3 except n = 2 for clade B) respectively. The EC50 values against HIV‑2 isolates (n = 4) from 3 to 120 nM in PBMCs. Ribavirin (50,000 nM) used in the treatment of chronic HCV infection decreased the anti-HIV‑1 activity of lamivudine by 3.5‑fold in MT‑4 cells.

Antiviral Activity in Combination with Other Antiviral Agents

Neither dolutegravir, abacavir, nor lamivudine were antagonistic to all tested anti-HIV agents. See full prescribing information for ZIAGEN (abacavir), TIVICAY (dolutegravir), and EPIVIR (lamivudine).

Resistance in Cell Culture

Dolutegravir: Dolutegravir-resistant viruses were selected in cell culture starting from different wild-type HIV‑1 strains and clades. Amino acid substitutions E92Q, G118R, S153F or Y, G193E or R263K emerged in different passages and conferred decreased susceptibility to dolutegravir of up to 4-fold.

Abacavir and Lamivudine: HIV-1 isolates with reduced susceptibility to the combination of abacavir and lamivudine have been selected in cell culture with amino acid substitutions K65R, L74V, Y115F, and M184V/I in HIV-1 RT. M184V or I substitutions resulted in high-level resistance to lamivudine and approximately 2-fold decrease in susceptibility to abacavir. Substitutions K65R, L74V, or Y115F with M184V or I conferred a 7- to 8-fold reduction in abacavir susceptibility, and combinations of three substitutions were required to confer more than an 8-fold reduction in susceptibility.

Resistance in Clinical Subjects

No subjects in the treatment arm receiving dolutegravir + EPZICOM in SINGLE (treatment- naive trial) had a detectable decrease in susceptibility to dolutegravir or background NRTIs in the resistance analysis subset (n = 11 with HIV-1 RNA >400 copies/mL at failure or last visit and having resistance data). Two virologic failure subjects in SINGLE had treatment-emergent G/D/E193D and G193G/E integrase substitutions at Week 84 and Week 108, respectively, and 1 subject with 275 copies/mL HIV-1 RNA had a treatment-emergent Q157Q/P integrase substitution detected at Week 24. None of these subjects had a corresponding decrease in dolutegravir susceptibility. No treatment-emergent genotypic resistance to abacavir and lamivudine, components of TRIUMEQ and TRIUMEQ PD, was observed in the arm receiving dolutegravir + EPZICOM in the SINGLE trial through Week 144. One ART-naïve subject receiving TRIUMEQ PD in the pediatric IMPAACT 2019 trial experienced confirmed virologic failure at Week 24 but subsequently suppressed to 76 copies/mL by Week 48 while on continued study treatment. The subject’s entry specimen (HIV-1 subtype AE) had the presence of baseline integrase substitution L74I polymorphism. Genotypic sequencing and phenotypic analyses failed at the confirmed virologic failure timepoint for this subject.

Cross-Resistance

Dolutegravir: Cross-resistance has been observed among INSTIs. The single INSTI-resistance substitutions T66K, I151L, and S153Y conferred a >2-fold decrease in dolutegravir susceptibility (range: 2.3-fold to 3.6-fold from reference). Combinations of multiple substitutions T66K/L74M, E92Q/N155H, G140C/Q148R, G140S/Q148H, R or K, Q148R/N155H, T97A/G140S/Q148, and substitutions at E138/G140/Q148 showed a >2-fold decrease in dolutegravir susceptibility (range: 2.5-fold to 21-fold from reference). In HIV-2 mutants, combinations of substitutions A153G/N155H/S163G and E92Q/T97A/N155H/S163D conferred 4-fold decreases in dolutegravir susceptibility, and E92Q/N155H and G140S/Q148R showed 8.5-fold and 17-fold decreases in dolutegravir susceptibility, respectively.

Abacavir and Lamivudine: Cross‑resistance has been observed among NRTIs. The combination of abacavir/lamivudine has demonstrated decreased susceptibility to viruses with a K65R substitution with or without an M184V/I substitution, viruses with L74V plus the M184V/I substitution, and viruses with thymidine analog mutation (TAM) substitutions (M41L, D67N, K70R, L210W, T215Y/F, K219 E/R/H/Q/N) plus M184V. An increasing number of TAMs is associated with a progressive reduction in abacavir susceptibility.

13 NONCLINICAL TOXICOLOGY

13.1 Carcinogenesis, Mutagenesis, Impairment of Fertility

Carcinogenicity

Dolutegravir: Two-year carcinogenicity studies in mice and rats were conducted with dolutegravir. Mice were administered doses of up to 500 mg/kg, and rats were administered doses of up to 50 mg/kg. In mice, no significant increases in the incidence of drug-related neoplasms were observed at the highest doses tested, resulting in dolutegravir AUC exposures approximately 26-fold higher than those in humans at the recommended dose of 50 mg once daily. In rats, no increases in the incidence of drug-related neoplasms were observed at the highest dose tested, resulting in dolutegravir AUC exposures 17-fold and 30-fold higher in males and females, respectively, than those in humans at the recommended dose of 50 mg once daily.

Abacavir: Abacavir was administered orally at 3 dosage levels to separate groups of mice and rats in 2‑year carcinogenicity studies. Results showed an increase in the incidence of malignant and non‑malignant tumors. Malignant tumors occurred in the preputial gland of males and the clitoral gland of females of both species, and in the liver of female rats. In addition, non‑malignant tumors also occurred in the liver and thyroid gland of female rats. These observations were made at systemic exposures in the range of 7 to 28 times the human exposure at the recommended dose of 600 mg.

Lamivudine: Long‑term carcinogenicity studies with lamivudine in mice and rats showed no evidence of carcinogenic potential at exposures up to 12 times (mice) and 57 times (rats) the human exposures at the recommended dose of 300 mg.

Mutagenicity

Dolutegravir: Dolutegravir was not genotoxic in the bacterial reverse mutation assay, mouse lymphoma assay, or in the in vivo rodent micronucleus assay.

Abacavir: Abacavir induced chromosomal aberrations both in the presence and absence of metabolic activation in an in vitro cytogenetic study in human lymphocytes. Abacavir was mutagenic in the absence of metabolic activation, although it was not mutagenic in the presence of metabolic activation in an L5178Y mouse lymphoma assay. Abacavir was clastogenic in males and not clastogenic in females in an in vivo mouse bone marrow micronucleus assay. Abacavir was not mutagenic in bacterial mutagenicity assays in the presence and absence of metabolic activation.

Lamivudine: Lamivudine was mutagenic in an L5178Y mouse lymphoma assay and clastogenic in a cytogenetic assay using cultured human lymphocytes. Lamivudine was not mutagenic in a microbial mutagenicity assay, in an in vitro cell transformation assay, in a rat micronucleus test, in a rat bone marrow cytogenetic assay, and in an assay for unscheduled DNA synthesis in rat liver.

Impairment of Fertility

Dolutegravir, abacavir, or lamivudine did not affect male or female fertility in rats at doses associated with exposures approximately 44, 9, or 112 times (respectively) higher than the exposures in humans at the doses of 50 mg, 600 mg, and 300 mg (respectively).

13.2 Animal Toxicology and/or Pharmacology

Myocardial degeneration was found in mice and rats following administration of abacavir for 2 years. The systemic exposures were equivalent to 7 to 21 times the expected systemic exposure in humans at a dose of 600 mg. The clinical relevance of this finding has not been determined.

14 CLINICAL STUDIES

14.1 Adult Subjects

The efficacy of TRIUMEQ is supported by data from a randomized, controlled trial (double-blind through 96 weeks and open-label phase from 96 to 144 weeks) in antiretroviral treatment-naive subjects, SINGLE (ING114467, NCT01263015) and other trials in treatment-naive subjects. See full prescribing information for TIVICAY. The efficacy of dolutegravir, in combination with at least two active background regimens in treatment-experienced, INSTI- naive subjects is supported by data from SAILING (ING111762, NCT01231516) (refer to the prescribing information for TIVICAY).

Treatment-Naive Subjects

In SINGLE, 833 subjects were randomized and received at least 1 dose of either TIVICAY 50 mg once daily with fixed-dose abacavir and lamivudine (EPZICOM) or fixed-dose efavirenz/emtricitabine/tenofovir disoproxil fumarate (ATRIPLA). At baseline, the median age of subjects was 35 years, 16% female, 32% non-white, 7% had hepatitis C co-infection (hepatitis B virus co-infection was excluded), 4% were CDC Class C (AIDS), 32% had HIV‑1 RNA >100,000 copies/mL, and 53% had CD4+ cell count <350 cells/mm^3; these characteristics were similar between treatment groups.

Week 144 (open-label-phase analysis which followed the Week 96 double-blind phase) outcomes for SINGLE are provided in Table 12.

Table 12. Virologic Outcomes of Randomized Treatment in SINGLE at 144 Weeks (Snapshot Algorithm)
 | TIVICAY + EPZICOM Once Daily; (n = 414) | ATRIPLA; Once Daily; (n = 419)
HIV‑1 RNA <50 copies/mL | 71% | 63%
Treatment differencea | 8.3% (95% CI: 2.0%, 14.6%)d
Virologic nonresponse | 10% | 7%
Data in window not <50 copies/mL | 4% | <1%
Discontinued for lack of efficacy | 3% | 3%
Discontinued for other reasons while not suppressed | 3% | 4%
No virologic data | 18% | 30%
Reasons
Discontinued study/study drug due to adverse event or deathb | 4% | 14%
Discontinued study/study drug for other reasonsc | 12% | 13%
Missing data during window but on study | 2% | 3%
Proportion (%) of Subjects with HIV‑1 RNA <50 copies/mL by Baseline Category
Plasma viral load (copies/mL)
≤100,000 | 73% | 64%
≥100,000 | 69% | 61%
Gender
Male | 72% | 66%
Female | 69% | 48%
Race
White | 72% | 71%
African American/African Heritage/Other | 71% | 47%
a Adjusted for pre-specified stratification factors.
b Includes subjects who discontinued due to an adverse event or death at any time point if this resulted in no virologic data on treatment during the analysis window.
c Other includes reasons such as withdrew consent, loss to follow-up, moved, and protocol deviation.
d The primary endpoint was assessed at Week 48 and the virologic success rate was 88% in the group receiving TIVICAY and 81% in the ATRIPLA group, with a treatment difference of 7.4% and 95% CI of (2.5%, 12.3%).

Treatment differences were maintained across baseline characteristics including baseline viral load, CD4+ cell count, age, gender, and race. The adjusted mean changes in CD4+ cell counts from baseline were 378 cells/mm^3 in the group receiving TIVICAY + EPZICOM and 332 cells/mm^3 for the ATRIPLA group at 144 weeks. The adjusted difference between treatment arms and 95% CI was 46.9 cells/mm^3 (15.6 cells/mm^3, 78.2 cells/mm^3) (adjusted for pre-specified stratification factors: baseline HIV‑1 RNA, and baseline CD4+ cell count).

Treatment-Experienced

In SAILING, there were 715 subjects included in the efficacy and safety analyses (see full prescribing information for TIVICAY). At Week 48, 71% of subjects randomized to TIVICAY plus background regimen versus 64% of subjects randomized to raltegravir plus background regimen had HIV‑1 RNA <50 copies/mL (treatment difference and 95% CI: 7.4% [0.7%, 14.2%]).

14.2 Pediatric Subjects

The efficacy of TRIUMEQ, TRIUMEQ PD and/or their individual components for the treatment of HIV-1 infection was evaluated in pediatric patients enrolled in the IMPAACT 2019 trial (NCT03760458), ARROW trial (NCT02028676) and IMPAACT P1093 trial (NCT01302847), as summarized below.

- TRIUMEQ and TRIUMEQ PD were evaluated in treatment-naive or treatment-experienced, HIV-1–infected subjects younger than 12 years in an open-label, multicenter clinical trial (IMPAACT 2019). Subjects were stratified by weight band and enrolled in one of five groups. Fifty-seven subjects, with a median age of 6.4 years (range: 1 to 11.3) and median weight of 17 kg (range: 8.2 to 39.3), received the recommended dose (determined by weight) and formulation, and contributed to the efficacy analysis at Week 48. At this timepoint, 79% of subjects achieved HIV-1 RNA less than 50 copies/mL and 95% achieved HIV-1 RNA less than 200 copies/mL (Snapshot algorithm).
- Abacavir and lamivudine once daily, in combination with a third antiretroviral drug, were evaluated in a randomized, multicenter trial (ARROW) in treatment-naive pediatric subjects with HIV-1 infection. Subjects randomized to once-daily dosing (n = 336) and who weighed at least 25 kg received abacavir 600 mg and lamivudine 300 mg, as either the single entities or as EPZICOM. At Week 96, 67% of subjects receiving abacavir and lamivudine once-daily in combination with a third antiretroviral drug, had HIV-1 RNA <80 copies/mL.
- Dolutegravir (TIVICAY or TIVICAY PD), in combination with other antiretroviral drugs, was evaluated in treatment-naive or treatment-experienced, INSTI-naive, HIV-1–infected subjects aged at least 4 weeks to 18 years in an ongoing open-label, multicenter, dose-finding clinical trial, IMPAACT P1093. Subjects were stratified by age from 4 weeks to younger than 18 years and enrolled in one of five age cohorts. Thirty-six subjects weighing at least 6 kg who received the recommended dose (determined by weight and age) and formulation contributed to the efficacy analysis at Week 48. At this timepoint, 72% (26/36) of subjects weighing at least 6 kg achieved HIV‑1 RNA <50 copies/mL (Snapshot algorithm).

16 HOW SUPPLIED/STORAGE AND HANDLING

TRIUMEQ tablets

TRIUMEQ tablets are purple, oval, film-coated, biconvex tablets debossed with “572 Tri” on one side and contain 600 mg of abacavir (as abacavir sulfate), 50 mg of dolutegravir (as dolutegravir sodium), and 300 mg lamivudine.

Bottle of 30 tablets with desiccant and child-resistant closure. NDC 49702-231-13.

Store and dispense in the original package, protect from moisture, and keep the bottle tightly closed. Do not remove desiccant.

Store at 20°C to 25°C (68°F to 77°F); excursions permitted between 15°C and 30°C (59°F to 86°F). [See USP Controlled Room Temperature].

TRIUMEQ PD tablets for oral suspension

TRIUMEQ PD tablets for oral suspension, are yellow, capsule-shaped, strawberry cream flavored, film-coated, biconvex tablets debossed with “SV WTU” on one side and contain 60 mg of abacavir (as abacavir sulfate), 5 mg of dolutegravir (as dolutegravir sodium), and 30 mg lamivudine.

Bottle of 90 tablets (NDC 49702-272-59) with desiccant and child-resistant closure. Each bottle is packaged as a kit (NDC 49702-258-37) with one 40-mL dosing cup.

Store at 20°C to 25°C (68°F to 77°F); excursions permitted between 15°C and 30°C (59°F to 86°F). [See USP Controlled Room Temperature]. Store and dispense in the original bottle, protect from moisture, and keep the bottle tightly closed. Do not remove desiccant.

17 PATIENT COUNSELING INFORMATION

Advise the patient to read the FDA-approved patient labeling (Medication Guide and Instructions for Use).

Drug Interactions

TRIUMEQ or TRIUMEQ PD may interact with many drugs; therefore, advise patients to report to their healthcare provider the use of any other prescription or nonprescription medication or herbal products, including St. John’s wort [see Contraindications (4), Warnings and Precautions (5.5), Drug Interactions (7)].

Hypersensitivity Reaction

Inform patients:

- that a Medication Guide and Warning Card summarizing the symptoms of the abacavir hypersensitivity reaction and other product information will be dispensed by the pharmacist with each new prescription and refill of TRIUMEQ or TRIUMEQ PD, and instruct the patient to read the Medication Guide and Warning Card every time to obtain any new information that may be present about TRIUMEQ or TRIUMEQ PD. The complete text of the Medication Guide is reprinted at the end of this document.
- to carry the Warning Card with them.
- how to identify a hypersensitivity reaction [see Warnings and Precautions (5.1), Medication Guide].
- that if they develop symptoms consistent with a hypersensitivity reaction they should call their healthcare provider right away to determine if they should stop taking TRIUMEQ or TRIUMEQ PD.
- that a hypersensitivity reaction can worsen and lead to hospitalization or death if TRIUMEQ or TRIUMEQ PD is not immediately discontinued.
- to not restart TRIUMEQ or TRIUMEQ PD or any other abacavir‑containing product following a hypersensitivity reaction because more severe symptoms can occur within hours and may include life‑threatening hypotension and death.
- that if they have a hypersensitivity reaction, they should dispose of any unused TRIUMEQ or TRIUMEQ PD to avoid restarting abacavir.
- that a hypersensitivity reaction is usually reversible if it is detected promptly and TRIUMEQ or TRIUMEQ PD is stopped right away.
- that if they have interrupted TRIUMEQ or TRIUMEQ PD for reasons other than symptoms of hypersensitivity (for example, those who have an interruption in drug supply), a serious or fatal hypersensitivity reaction may occur with reintroduction of abacavir.
- to not restart TRIUMEQ or TRIUMEQ PD or any other abacavir‑containing product without medical consultation and only if medical care can be readily accessed by the patient or others.
- to not restart TRIUMEQ or TRIUMEQ PD or any other dolutegravir-containing product following a hypersensitivity reaction to TRIUMEQ or TRIUMEQ PD.

Hepatotoxicity

Inform patients that hepatotoxicity has been reported with dolutegravir, a component of TRIUMEQ and TRIUMEQ PD [see Warnings and Precautions (5.3), Adverse Reactions (6.1)]. Inform patients that monitoring for hepatotoxicity during therapy with TRIUMEQ or TRIUMEQ PD is recommended.

Severe Acute Exacerbations of Hepatitis in Patients with HBV Co-infection

Advise all patients with HIV-1 to be tested for the presence of HBV prior to or when initiating TRIUMEQ or TRIUMEQ PD. Advise patients co‑infected with HIV‑1 and HBV that worsening of liver disease has occurred in some cases when treatment with lamivudine was discontinued. Advise patients to discuss any changes in regimen with their physician [see Warnings and Precautions (5.2)].

Lactic Acidosis/Hepatomegaly

Inform patients that some HIV medicines, including TRIUMEQ and TRIUMEQ PD, can cause a rare, but serious condition called lactic acidosis with liver enlargement (hepatomegaly) [see Boxed Warning, Warnings and Precautions (5.4)].

Immune Reconstitution Syndrome

Advise patients to inform their healthcare provider immediately of any signs and symptoms of infection as inflammation from previous infection may occur soon after combination antiretroviral therapy, including when TRIUMEQ or TRIUMEQ PD is started [see Warnings and Precautions (5.6)].

TRIUMEQ Tablets and TRIUMEQ PD Tablets for Oral Suspension Are Not Bioequivalent

Advise patients that TRIUMEQ and TRIUMEQ PD are not bioequivalent and are not substitutable on a milligram-per-milligram basis. Advise patients or their care provider that patients switching from the tablets for oral suspension to the tablets must adjust the dose [see Dosage and Administration (2.3) and Warnings and Precautions (5.7)].

Pregnancy Registry

Inform patients that there is an antiretroviral pregnancy registry to monitor fetal outcomes in those exposed to TRIUMEQ during pregnancy [see Use in Specific Populations (8.1)].

Lactation

Inform individuals with HIV-1 infection that the potential risks of breastfeeding include: (1) HIV-1 transmission (in HIV-1–negative infants), (2) developing viral resistance (in HIV-1–positive infants), and (3) adverse reactions in a breastfed infant similar to those seen in adults [see Use in Specific Populations (8.2)].

Administration Instructions

To avoid a dosing error from using the wrong formulation of TRIUMEQ, strongly advise patients and caregivers to visually inspect the tablets to verify the correct formulation each time the prescription is filled [see Dosage and Administration (2), Warnings and Precautions (5.7), How Supplied/Storage and Handling (16)].

Inform patients and caregivers that TRIUMEQ PD tablets for oral suspension should be dispersed in drinking water and should not be chewed, cut, crushed, or swallowed whole [see Dosage and Administration (2.5)]. Inform patients and caregivers that an appropriate-sized syringe may be used to administer the oral suspension if the patient is unable to use the supplied cup [see Dosage and Administration (2.5)].

Instruct patients and caregivers that if a dose of TRIUMEQ or TRIUMEQ PD is missed, to take it as soon as they remember. Advise patients and caregivers not to double the next dose or take more than the prescribed dose [see Dosage and Administration (2)].

Availability of Medication Guide

Instruct patients and caregivers to read the Medication Guide before starting TRIUMEQ or TRIUMEQ PD and to re-read it each time the prescription is renewed. Instruct patients to inform their physician or pharmacist if they develop any unusual symptom, or if any known symptom persists or worsens.

Storage

Instruct patients and caregivers to store TRIUMEQ and TRIUMEQ PD tablets for oral suspension in the original package, protect from moisture, and keep the bottle tightly closed. Do not remove desiccant.

EPIVIR, EPZICOM, TIVICAY, TIVICAY PD, TRIUMEQ, TRIUMEQ PD, and ZIAGEN are trademarks owned by or licensed to the ViiV Healthcare group of companies.

EPIVIR-HBV is a trademark owned by or licensed to the GSK group of companies.

The other brands listed are trademarks owned by or licensed to their respective owners and are not owned by or licensed to the ViiV Healthcare group of companies. The makers of these brands are not affiliated with and do not endorse the ViiV Healthcare group of companies or its products.

Manufactured for:

ViiV Healthcare

Durham, NC 27701

©2025 ViiV Healthcare group of companies or its licensor.

TRM:19PI

MEDICATION GUIDE

TRIUMEQ (TRI-u-meck)

(abacavir, dolutegravir, and lamivudine)

tablets

TRIUMEQ PD (TRI-u-meck Pe De)

(abacavir, dolutegravir, and lamivudine)

tablets for oral suspension

What is the most important information I should know about TRIUMEQ and TRIUMEQ PD?

TRIUMEQ and TRIUMEQ PD can cause serious side effects, including:

- Serious allergic reactions (hypersensitivity reaction) that can cause death have happened with TRIUMEQ or TRIUMEQ PD and other abacavir-containing products. Your risk of this allergic reaction to abacavir is much higher if you have a gene variation called HLA‑B*5701. Your healthcare provider can determine with a blood test if you have this gene variation.
If you get a symptom from 2 or more of the following groups while taking TRIUMEQ or TRIUMEQ PD, call your healthcare provider right away to find out if you should stop taking TRIUMEQ or TRIUMEQ PD.

Symptom(s)

Group 1

Fever

Group 2

Rash

Group 3

Nausea, vomiting, diarrhea, abdominal (stomach area) pain

Group 4

Generally ill feeling, extreme tiredness, or achiness

Group 5

Shortness of breath, cough, sore throat

A list of these symptoms is on the Warning Card your pharmacist gives you. Carry this Warning Card with you at all times.

If you stop TRIUMEQ or TRIUMEQ PD because of an allergic reaction, never take TRIUMEQ, TRIUMEQ PD (abacavir, dolutegravir and lamivudine), or any other medicine that contains abacavir or dolutegravir (DOVATO, EPZICOM, JULUCA, TIVICAY, TIVICAY PD, TRIZIVIR, or ZIAGEN) again.

- If you have an allergic reaction, dispose of any unused TRIUMEQ or TRIUMEQ PD. Ask your pharmacist how to properly dispose of medicines.
- If you take TRIUMEQ, TRIUMEQ PD or any other abacavir‑containing medicine again after you have had an allergic reaction, within hours you may get life‑threatening symptoms that may include very low blood pressure or death.
- If you stop TRIUMEQ or TRIUMEQ PD for any other reason, even for a few days, and you are not allergic to TRIUMEQ or TRIUMEQ PD, talk with your healthcare provider before taking it again. Taking TRIUMEQ or TRIUMEQ PD again can cause a serious allergic or life‑threatening reaction, even if you never had an allergic reaction to it before.

If your healthcare provider tells you that you can take TRIUMEQ or TRIUMEQ PD again, start taking it when you are around medical help or people who can call a healthcare provider if you need one.

- Worsening of Hepatitis B virus (HBV) infection. Your healthcare provider will test you for HBV infection before you start treatment with TRIUMEQ or TRIUMEQ PD. If you have HBV infection and take TRIUMEQ or TRIUMEQ PD, your HBV may get worse (flare-up) if you stop taking TRIUMEQ or TRIUMEQ PD. A “flare-up” is when your HBV infection suddenly returns in a worse way than before.
  - Do not run out of TRIUMEQ or TRIUMEQ PD. Refill your prescription or talk to your healthcare provider before your TRIUMEQ or TRIUMEQ PD is all gone.
  - Do not stop TRIUMEQ or TRIUMEQ PD without first talking to your healthcare provider.
  - If you stop taking TRIUMEQ or TRIUMEQ PD, your healthcare provider will need to check your health often and do blood tests regularly for several months to check your liver function and monitor your HBV infection. It may be necessary to give you a medicine to treat hepatitis B. Tell your healthcare provider about any new or unusual symptoms you may have after you stop taking TRIUMEQ or TRIUMEQ PD.
- Resistant HBV. If you have human immunodeficiency virus-1 (HIV-1) and HBV, the HBV can change (mutate) during your treatment with TRIUMEQ or TRIUMEQ PD and become harder to treat (resistant). Your healthcare provider may give you other medicines to treat HBV infection if you have HIV-1 and HBV infections and take TRIUMEQ or TRIUMEQ PD.
- For more information about side effects, see “What are the possible side effects of TRIUMEQ or TRIUMEQ PD?”

What is TRIUMEQ and TRIUMEQ PD?

TRIUMEQ and TRIUMEQ PD are prescription medicines used to treat HIV-1 infection in adults and children who are at least 3 months of age and weigh at least 13.2 pounds (6 kg).

HIV-1 is the virus that causes Acquired Immune Deficiency Syndrome (AIDS).

TRIUMEQ and TRIUMEQ PD contain the prescription medicines abacavir, dolutegravir, and lamivudine.

- TRIUMEQ or TRIUMEQ PD should not be used by itself in people who have resistance to certain types of medicines.

It is not known if TRIUMEQ PD is safe and effective in children who are less than 3 months of age or weigh less than 13.2 pounds (6 kg).

Do not take TRIUMEQ or TRIUMEQ PD if you:

- have a certain type of gene variation called the HLA‑B*5701 allele. Your healthcare provider will test you for this before prescribing treatment with TRIUMEQ or TRIUMEQ PD.
- are allergic to abacavir, dolutegravir, lamivudine, or any of the ingredients in TRIUMEQ or TRIUMEQ PD. See the end of this Medication Guide for a complete list of ingredients in TRIUMEQ and TRIUMEQ PD.
- take dofetilide. Taking TRIUMEQ or TRIUMEQ PD and dofetilide can cause side effects that may be serious or life-threatening.
- have certain liver problems.

Before you take TRIUMEQ or TRIUMEQ PD, tell your healthcare provider about all of your medical conditions, including if you:

- have been tested and know whether or not you have a particular gene variation called HLA‑B*5701.
- have or have had liver problems, including hepatitis B or C virus infection.
- have kidney problems.
- have heart problems, smoke, or have diseases that increase your risk of heart disease such as high blood pressure, high cholesterol, or diabetes.
- drink alcohol or take medicines that contain alcohol.
- are pregnant or plan to become pregnant. Talk to your healthcare provider about the benefits and risks of treatment with TRIUMEQ during pregnancy.

Pregnancy Registry. There is a pregnancy registry for those who take TRIUMEQ during pregnancy. The purpose of this registry is to collect information about the health of you and your baby. Talk with your healthcare provider about how you can take part in this registry.

- are breastfeeding or plan to breastfeed. TRIUMEQ passes to your baby in your breast milk. Talk with your healthcare provider about the following risks to your baby from breastfeeding during treatment with TRIUMEQ:
  - the HIV-1 virus may pass to your baby if your baby does not have HIV-1 infection.
  - the HIV-1 virus may become harder to treat if your baby has HIV-1 infection.
  - your baby may get side effects from TRIUMEQ.

Tell your healthcare provider about all the medicines you take, including prescription and over-the-counter medicines, vitamins, and herbal supplements.

Some medicines interact with TRIUMEQ or TRIUMEQ PD. Keep a list of your medicines to show your healthcare provider and pharmacist when you get a new medicine.

- You can ask your healthcare provider or pharmacist for a list of medicines that interact with TRIUMEQ or TRIUMEQ PD.
- Do not start taking a new medicine without telling your healthcare provider. Your healthcare provider can tell you if it is safe to take TRIUMEQ or TRIUMEQ PD with other medicines.

How should I take TRIUMEQ or TRIUMEQ PD?

Read the Instructions for Use at the end of this Medication Guide for detailed instructions on how to prepare a dose of TRIUMEQ PD tablets for oral suspension.

- Take TRIUMEQ or TRIUMEQ PD exactly as your healthcare provider tells you to take it.
- Do not change your dose, switch medicines or stop taking TRIUMEQ or TRIUMEQ PD without talking with your healthcare provider first.
- TRIUMEQ tablets are not the same as TRIUMEQ PD tablets for oral suspension and cannot be substituted for each other. Check to make sure you receive the correct dosage form each time you or your child’s prescription is filled to avoid using the wrong medicine.
- Your child’s healthcare provider will prescribe TRIUMEQ or TRIUMEQ PD based on your child’s weight.
- TRIUMEQ PD tablets for oral suspension should be dispersed in drinking water.
- Do not chew, cut, or crush TRIUMEQ tablets or TRIUMEQ PD tablets for oral suspension. Do not swallow TRIUMEQ PD tablets for oral suspension whole.
- TRIUMEQ or TRIUMEQ PD may be taken with or without food.
- If you take antacids, laxatives, or other medicines that contain aluminum, magnesium, or buffered medicines, TRIUMEQ or TRIUMEQ PD should be taken at least 2 hours before or 6 hours after you take these medicines.
- If you need to take iron or calcium supplements, or multivitamin supplements that contain iron or calcium, by mouth during treatment with TRIUMEQ or TRIUMEQ PD:
  - If you take TRIUMEQ or TRIUMEQ PD with food, you may take these supplements at the same time that you take TRIUMEQ or TRIUMEQ PD.
  - If you do not take TRIUMEQ or TRIUMEQ PD with food, take TRIUMEQ or TRIUMEQ PD at least 2 hours before or 6 hours after you take these supplements.
- If you miss a dose of TRIUMEQ or TRIUMEQ PD, take it as soon as you remember. Do not take 2 doses at the same time or take more than your healthcare provider tells you to take.
- Stay under the care of a healthcare provider during treatment with TRIUMEQ or TRIUMEQ PD.
- Do not run out of TRIUMEQ or TRIUMEQ PD. The virus in your blood may increase and the virus may become harder to treat. When your supply starts to run low, get more from your healthcare provider or pharmacy.
- If you take too much TRIUMEQ or TRIUMEQ PD, call your healthcare provider or go to the nearest hospital emergency room right away.

What are the possible side effects of TRIUMEQ or TRIUMEQ PD?

TRIUMEQ or TRIUMEQ PD can cause serious side effects, including:

- See “What is the most important information I should know about TRIUMEQ and TRIUMEQ PD?”
- Liver problems. People with a history of hepatitis B or C virus may have an increased risk of developing new or worsening changes in certain liver function tests during treatment with TRIUMEQ or TRIUMEQ PD. Liver problems including liver failure have also happened with TRIUMEQ or TRIUMEQ PD in people without a history of liver disease or other risk factors. Liver failure resulting in liver transplant has also been reported with TRIUMEQ. Your healthcare provider may do blood tests to check your liver. Call your healthcare provider right away if you develop any of the signs or symptoms of liver problems listed below.

- your skin or the white part of your eyes turns yellow (jaundice)
- dark or “tea-colored” urine
- light colored stools (bowel movements)

- loss of appetite
- nausea or vomiting
- pain, aching, or tenderness on the right side of your stomach area

- Too much lactic acid in your blood (lactic acidosis). Too much lactic acid is a serious medical emergency that can lead to death. Call your healthcare provider right away if you get any of the following symptoms that could be signs of lactic acidosis:

- feel very weak or tired
- unusual (not normal) muscle pain
- trouble breathing
- stomach pain with nausea and vomiting

- feel cold, especially in your arms and legs
- feel dizzy or lightheaded
- have a fast or irregular heartbeat

- Lactic acidosis can also lead to severe liver problems, which can lead to death. Your liver may become large (hepatomegaly), and you may develop fat in your liver (steatosis). Call your healthcare provider right away if you get any of the signs or symptoms of liver problems which are listed above under “Liver problems”.
- You may be more likely to get lactic acidosis or severe liver problems if you are female or very overweight (obese).
- Changes in your immune system (Immune Reconstitution Syndrome) can happen when you start taking HIV-1 medicines. Your immune system may get stronger and begin to fight infections that have been hidden in your body for a long time. Tell your healthcare provider right away if you start having new symptoms after you start taking TRIUMEQ or TRIUMEQ PD.
- Heart attack. Some HIV-1 medicines including TRIUMEQ or TRIUMEQ PD may increase your risk of heart attack.
- The most common side effects of TRIUMEQ include:

- trouble sleeping

- headache

- tiredness

These are not all the possible side effects of TRIUMEQ or TRIUMEQ PD.

Call your doctor for medical advice about side effects. You may report side effects to FDA at 1‑800‑FDA‑1088.

How should I store TRIUMEQ or TRIUMEQ PD?

- Store TRIUMEQ and TRIUMEQ PD at room temperature between 68°F to 77°F (20°C to 25°C) in the original bottle. Keep the bottle tightly closed and protect it from moisture.
- The bottle of TRIUMEQ and TRIUMEQ PD contains a desiccant packet to help keep your medicine dry (protect it from moisture). Do not remove the desiccant packet from the bottle.

Keep TRIUMEQ, TRIUMEQ PD, and all medicines out of the reach of children.

General information about the safe and effective use of TRIUMEQ or TRIUMEQ PD.

Medicines are sometimes prescribed for purposes other than those listed in a Medication Guide. Do not use TRIUMEQ or TRIUMEQ PD for a condition for which it was not prescribed. Do not give TRIUMEQ or TRIUMEQ PD to other people, even if they have the same symptoms that you have. It may harm them. You can ask your pharmacist or healthcare provider for information about TRIUMEQ or TRIUMEQ PD that is written for health professionals.

What are the ingredients in TRIUMEQ and TRIUMEQ PD?

Active ingredients: abacavir, dolutegravir, and lamivudine

Inactive ingredients:

TRIUMEQ tablets: D-mannitol, magnesium stearate, microcrystalline cellulose, povidone, and sodium starch glycolate. Tablet film‑coating contains: iron oxide black, iron oxide red, macrogol/PEG, polyvinyl alcohol–part hydrolyzed, talc, and titanium oxide.

TRIUMEQ PD tablets for oral suspension: acesulfame potassium, crospovidone, mannitol, microcrystalline cellulose, povidone K29/32, silicified microcrystalline cellulose, sodium starch glycolate, sodium stearyl fumarate, strawberry cream flavor, and sucralose.

Tablet film‑coating contains: ferric oxide yellow, macrogol/PEG, polyvinyl alcohol-part hydrolyzed, talc, and titanium dioxide.

Manufactured for:

ViiV Healthcare

Durham, NC 27701

DOVATO, EPZICOM, JULUCA, TIVICAY, TIVICAY PD, TRIUMEQ, TRIUMEQ PD, TRIZIVIR, and ZIAGEN are trademarks owned by or licensed to the ViiV Healthcare group of companies.

©2024 ViiV Healthcare group of companies or its licensor. TRM:17MG

For more information go to www.TRIUMEQ.com or call 1-877-844-8872.

This Medication Guide has been approved by the U.S. Food and Drug Administration.

Revised: 4/2024

INSTRUCTIONS FOR USE

TRIUMEQ PD (TRI-u-meck Pe De)

(abacavir, dolutegravir, and lamivudine)

tablets for oral suspension

This Instructions for Use contains information on how to take TRIUMEQ PD.

Read this Instructions for Use before your child starts taking TRIUMEQ PD for the first time and each time you get a refill. There may be new information. This information does not take the place of talking to your healthcare provider about your child’s medical condition or treatment. Talk to your healthcare provider or pharmacist if you have any questions on how to prepare or give the prescribed dose of TRIUMEQ PD.

Important Information You Need to Know Before Giving TRIUMEQ PD

- Give TRIUMEQ PD exactly as your healthcare provider tells you.
- Each time you receive your child’s prescription, check the bottle to make sure that you received TRIUMEQ PD. TRIUMEQ tablets are not the same as TRIUMEQ PD tablets for oral suspension and cannot be substituted for each other. Contact your pharmacist or healthcare provider if you did not receive the correct dosage form.
- Do not chew, cut, crush, or swallow whole the tablets for oral suspension.
- If you forget to give a dose of TRIUMEQ PD, give it as soon as you remember. Do not give 2 doses at the same time or give more than your healthcare provider has prescribed.
- If your child does not or cannot take the full dose, call your healthcare provider.
- If you give too much TRIUMEQ PD, get emergency medical help right away.
- For more information about TRIUMEQ PD, read the Medication Guide.

Your pack contains:

- A bottle containing 90 TRIUMEQ PD tablets for oral suspension
- Dosing cup

Supply not included in the pack

- Oral syringe (optional)

If your child cannot use the supplied dosing cup, you may need an oral syringe to give the medicine. Talk to your healthcare provider for advice about the size of oral syringe you should use to give TRIUMEQ PD.

You will also need:

- Clean drinking water.

Preparing to Give TRIUMEQ PD

Step 1. Pour water

Figure A

- Pour clean drinking water into the cup.
The Water Volume Guide in Figure A shows the amount of water needed for the prescribed dose
See Figure A.

Use drinking water only.

Do not use any other drink or food to prepare the dose.

TRIUMEQ PD tablets for oral suspension must be dispersed in drinking water before you give them to your child.

Step 2. Prepare the medicine

Figure B Figure C

- Add the prescribed number of tablet(s) to the water. See Figure B.
- Swirl the cup gently for 1 to 2 minutes to disperse the tablet(s). The medicine will become cloudy. Take care not to spill any of the medicine. See Figure C.
- Check that the medicine is ready. If there are any lumps of tablet, swirl the cup until they are gone.

If you spill any medicine, clean up the spill.

Throw away the rest of the prepared medicine and make a new dose.

You must give the dose of medicine within 30 minutes of preparing the dose. If it has been more than 30 minutes, wash away all the dose in the cup using water and prepare a new dose of medicine.

Giving TRIUMEQ PD

Step 3. Give the medicine

Figure D

- Make sure that the child is upright. Give all the prepared medicine to the child. See Figure D.
- Add another 15 mL or less of drinking water to the cup, swirl, and give it all to the child.
- Repeat if any medicine remains in the cup to make sure the child gets the full dose.

Figure E Figure F

- Place the tip of the oral syringe into the prepared medicine and draw up all the medicine into the oral syringe by pulling up on the plunger. See Figure E.
- Place the tip of the oral syringe against the inside of the child’s cheek. Gently push down the plunger to give the dose slowly. See Figure F.
- Add another 15 mL or less of drinking water to the cup and swirl. Draw up the remaining medicine into the oral syringe and give it all to the child.
- Repeat if any medicine remains in the oral syringe to make sure the child gets the full dose.

Allow time for the medicine to be swallowed

Cleaning the Dosing Items

Step 4. Clean the dosing items you used to give TRIUMEQ PD

Figure G Figure H

- Wash all the dosing items with water. See Figure G and Figure H.
- If using and oral syringe, pull the plunger out of the syringe parts separately in water. Allow parts to dry completely before reassembling and storing. See Figure H.
- All parts will need to be clean before preparing the next dose.

Storing TRIUMEQ PD

- Store TRIUMEQ PD tablets for oral suspension at room temperature between 68°F to 77°F (20°C to 25°C) in the original bottle. Keep the bottle tightly closed and protect from moisture.
- The TRIUMEQ PD bottle contains a desiccant packet to help keep your medicine dry (protect it from moisture). Do not remove the desiccant packet from the bottle.

Keep TRIUMEQ PD and all medicines out of the reach of children.

Disposing of TRIUMEQ PD

When all the tablets in the bottle have been taken or are no longer needed, throw away the bottle, cup, and oral syringe. Dispose of them using your local household waste guidelines.

You will get a new cup in your next pack.

Manufactured for:

ViiV Healthcare

Durham, NC 27701

Trademarks are owned by or licensed to the ViiV Healthcare group of companies.

©2023 ViiV Healthcare group of companies or its licensor.

TRM:3IFU

This Instructions for Use has been approved by the U.S. Food and Drug Administration.

Revised: 6/2023

PACKAGE LABEL

PRINICPAL DISPLAY PANEL

NDC 49702-231-13

Triumeq

(abacavir, dolutegravir, and lamivudine) Tablets

600 mg/50 mg/300 mg

Rx only

Triumeq and Triumeq PD are not interchangeable.

Notice ot Authorized Dispenser:

Each time TRIUMEQ is dispensed, give the patient a Medication Guide and Warning Card.

30 Tablets

Each film-coated tablet contains 600 mg of abacavir (equivalent to 702 mg of abacavir sulfate), 50 mg of dolutegravir (equivalent to 52.6 mg of dolutegravir sodium), and 300 mg of lamivudine.

Store at 20°C to 25°C (68°F to 77°F); excursions permitted to 15° to 30°C (59° to 86°F) [See USP Controlled Room Temperature].

Keep bottle tightly closed; protect from moisture. Do not remove desiccant.

This package is child-resistant. Keep out of reach of children. See prescribing information for dosage information.

Do not accept if membrane seal under cap is missing or broken.

Manufactured for:

ViiV Healthcare

Durham, NC 27701

Trademarks owned or licensed by ViiV Healthcare.

©2023 ViiV Healthcare or licensor.

www.triumeq.com

Rev. 1/23
62000000084540

PACKAGE LABEL

PRINICPAL DISPLAY PANEL

NDC 49702-258-37

Triumeq PD

(abacavir, dolutegravir, and lamivudine)

Tablets of Oral Suspension

60 mg/5 mg/30 mg

Rx Only

Triumeq and Triumeq PD are not interchangeable.

Notice of Authorized Dispenser:

Each time Triumeq PD is dispensed, give the patient a Medication Guide and the Warning Card from the carton.

See prescribing information for dosage information.

Contents:

- 1 Bottle of 90 tablets
- 1 Dosing cup
- Prescribing Information
- Medication Guide
- Instructions for Use

90 tablets

ViiV Healthcare

©2022 ViiV Healthcare group of companies or its licensor.

Made in UK

62000000084619 Rev. 12/22